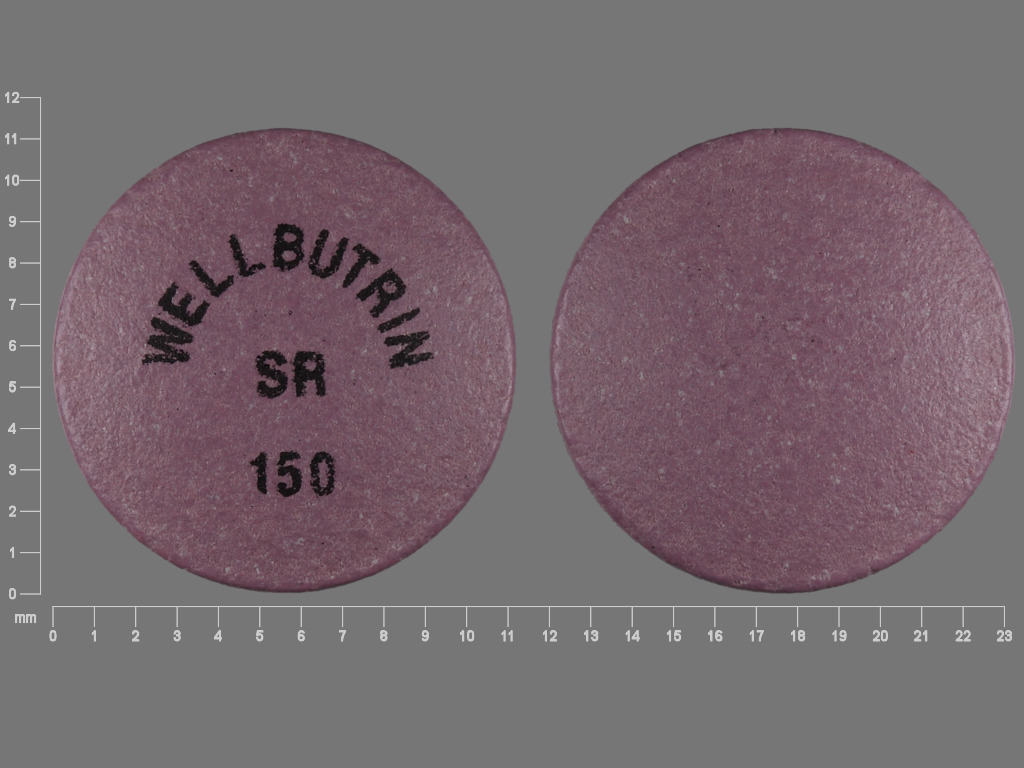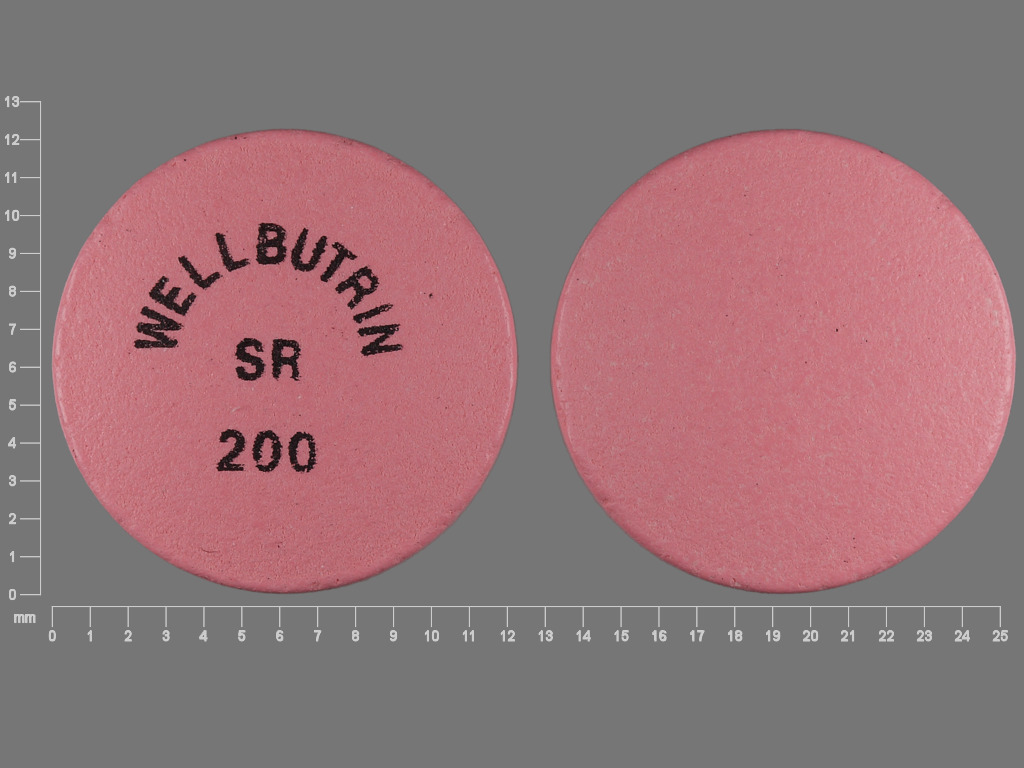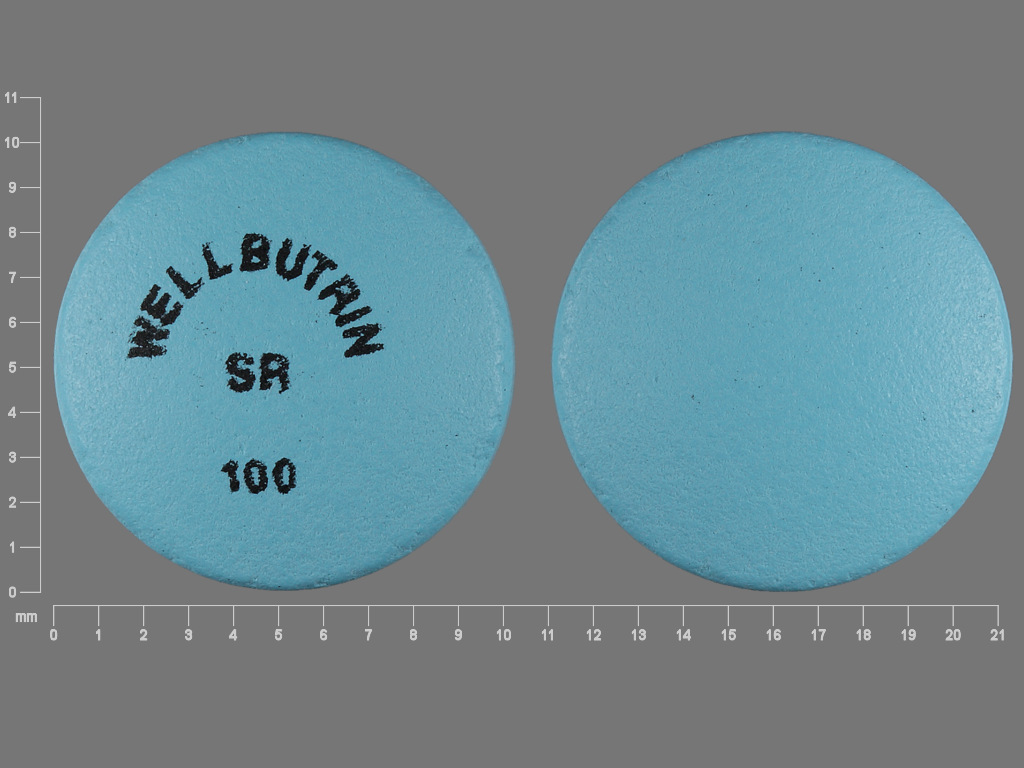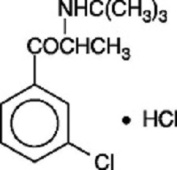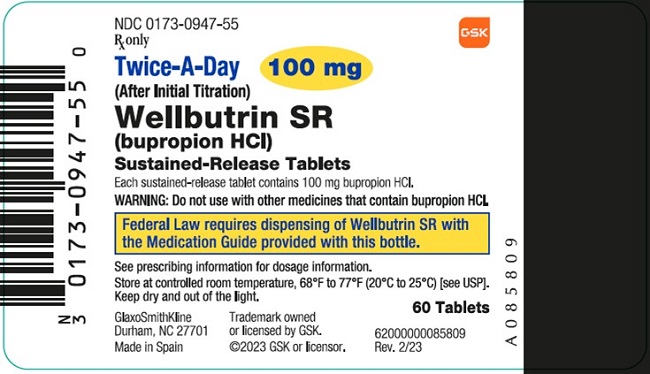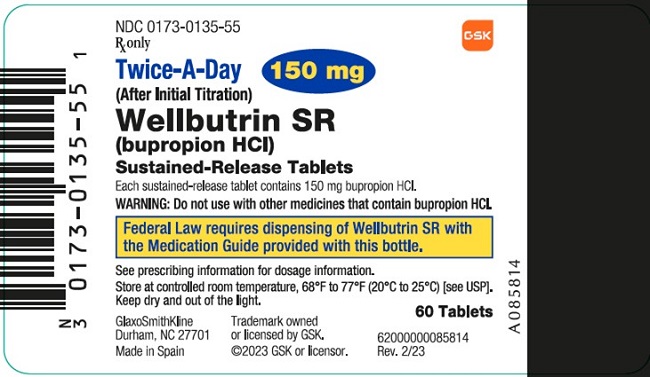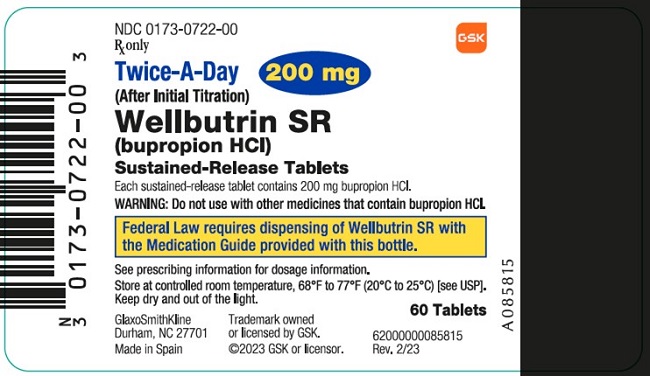 DRUG LABEL: WELLBUTRIN
NDC: 0173-0947 | Form: TABLET, FILM COATED
Manufacturer: GlaxoSmithKline LLC
Category: prescription | Type: HUMAN PRESCRIPTION DRUG LABEL
Date: 20251105

ACTIVE INGREDIENTS: BUPROPION HYDROCHLORIDE 100 mg/1 1
INACTIVE INGREDIENTS: CARNAUBA WAX; CYSTEINE HYDROCHLORIDE; HYPROMELLOSE, UNSPECIFIED; MAGNESIUM STEARATE; MICROCRYSTALLINE CELLULOSE; POLYETHYLENE GLYCOL, UNSPECIFIED; POLYSORBATE 80; TITANIUM DIOXIDE; FD&C BLUE NO. 1

HIGHLIGHTS OF PRESCRIBING INFORMATION

These highlights do not include all the information needed to use WELLBUTRIN SR safely and effectively. See full prescribing information for WELLBUTRIN SR.
WELLBUTRIN SR (bupropion hydrochloride) sustained-release tablets, for oral use
Initial U.S. Approval: 1985

WARNING: SUICIDAL THOUGHTS AND BEHAVIORS

See full prescribing information for complete boxed warning.

- Increased risk of suicidal thinking and behavior in children, adolescents and young adults taking antidepressants. (5.1)
- Monitor for worsening and emergence of suicidal thoughts and behaviors. (5.1)

1 INDICATIONS AND USAGE

WELLBUTRIN SR is an aminoketone antidepressant, indicated for the treatment of major depressive disorder (MDD). (1)

2 DOSAGE AND ADMINISTRATION

- Starting dose: 150 mg/day. (2.1)
- General: Increase dose gradually to reduce seizure risk. (2.1, 5.3)
- After 3 days, may increase the dose to 300 mg/day, given as 150 mg twice daily at an interval of at least 8 hours. (2.1)
- Usual target dose: 300 mg/day as 150 mg twice daily. (2.1)
- Maximum dose: 400 mg/day, given as 200 mg twice daily, for patients not responding to 300 mg/day. (2.1)
- Periodically reassess the dose and need for maintenance treatment. (2.1)
- Moderate to severe hepatic impairment: 100 mg daily or 150 mg every other day. (2.2, 8.7)
- Mild hepatic impairment: Consider reducing the dose and/or frequency of dosing. (2.2, 8.7)
- Renal impairment: Consider reducing the dose and/or frequency. (2.3, 8.6)

3 DOSAGE FORMS AND STRENGTHS

Tablets: 100 mg, 150 mg, 200 mg. (3)

4 CONTRAINDICATIONS

- Seizure disorder. (4, 5.3)
- Current or prior diagnosis of bulimia or anorexia nervosa. (4, 5.3)
- Abrupt discontinuation of alcohol, benzodiazepines, barbiturates, antiepileptic drugs. (4, 5.3)
- Monoamine Oxidase Inhibitors (MAOIs): Do not use MAOIs intended to treat psychiatric disorders with WELLBUTRIN SR or within 14 days of stopping treatment with WELLBUTRIN SR. Do not use WELLBUTRIN SR within 14 days of stopping an MAOI intended to treat psychiatric disorders. In addition, do not start WELLBUTRIN SR in a patient who is being treated with linezolid or intravenous methylene blue. (4, 7.6)
- Known hypersensitivity to bupropion or other ingredients of WELLBUTRIN SR. (4, 5.8)

5 WARNINGS AND PRECAUTIONS

- Neuropsychiatric adverse events during smoking cessation: Postmarketing reports of serious or clinically significant neuropsychiatric adverse events have included changes in mood (including depression and mania), psychosis, hallucinations, paranoia, delusions, homicidal ideation, aggression, hostility, agitation, anxiety, and panic, as well as suicidal ideation, suicide attempt, and completed suicide. Observe patients attempting to quit smoking with bupropion for the occurrence of such symptoms and instruct them to discontinue bupropion and contact a healthcare provider if they experience such adverse events. (5.2)
- Seizure risk: The risk is dose-related. Can minimize risk by gradually increasing the dose and limiting daily dose to 400 mg. Discontinue if seizure occurs. (4, 5.3, 7.3)
- Hypertension: WELLBUTRIN SR can increase blood pressure. Monitor blood pressure before initiating treatment and periodically during treatment. (5.4)
- Activation of mania/hypomania: Screen patients for bipolar disorder and monitor for these symptoms. (5.5)
- Psychosis and other neuropsychiatric reactions: Instruct patients to contact a healthcare professional if such reactions occur. (5.6)
- Angle-closure glaucoma: Angle-closure glaucoma has occurred in patients with untreated anatomically narrow angles treated with antidepressants. (5.7)

6 ADVERSE REACTIONS

Most common adverse reactions (incidence ≥5% and ≥2% more than placebo rate) are: headache, dry mouth, nausea, insomnia, dizziness, pharyngitis, constipation, agitation, anxiety, abdominal pain, tinnitus, tremor, palpitation, myalgia, sweating, rash, and anorexia. (6.1)

To report SUSPECTED ADVERSE REACTIONS, contact GlaxoSmithKline at 1-888-825-5249 or FDA at 1-800-FDA-1088 or www.fda.gov/medwatch.

7 DRUG INTERACTIONS

- CYP2B6 inducers: Dose increase may be necessary if coadministered with CYP2B6 inducers (e.g., ritonavir, lopinavir, efavirenz, carbamazepine, phenobarbital, and phenytoin) based on clinical response, but should not exceed the maximum recommended dose. (7.1)
- Drugs metabolized by CYP2D6: Bupropion inhibits CYP2D6 and can increase concentrations of: antidepressants (e.g., venlafaxine, nortriptyline, imipramine, desipramine, paroxetine, fluoxetine, sertraline), antipsychotics (e.g., haloperidol, risperidone, thioridazine), beta-blockers (e.g., metoprolol), and Type 1C antiarrhythmics (e.g., propafenone, flecainide). Consider dose reduction when using with bupropion. (7.2)
- Digoxin: May decrease plasma digoxin levels. Monitor digoxin levels. (7.2)
- Drugs that lower seizure threshold: Dose WELLBUTRIN SR with caution. (5.3, 7.3)
- Dopaminergic drugs (levodopa and amantadine): CNS toxicity can occur when used concomitantly with WELLBUTRIN SR. (7.4)
- MAOIs: Increased risk of hypertensive reactions can occur when used concomitantly with WELLBUTRIN SR. (7.6)
- Drug-laboratory test interactions: WELLBUTRIN SR can cause false-positive urine test results for amphetamines. (7.7)

FULL PRESCRIBING INFORMATION

WARNING: SUICIDAL THOUGHTS AND BEHAVIORS

SUICIDALITY AND ANTIDEPRESSANT DRUGS

Antidepressants increased the risk of suicidal thoughts and behavior in children, adolescents, and young adults in short-term trials. These trials did not show an increase in the risk of suicidal thoughts and behavior with antidepressant use in subjects over age 24; there was a reduction in risk with antidepressant use in subjects aged 65 and older [see Warnings and Precautions (5.1)].

In patients of all ages who are started on antidepressant therapy, monitor closely for worsening, and for emergence of suicidal thoughts and behaviors. Advise families and caregivers of the need for close observation and communication with the prescriber [see Warnings and Precautions (5.1)].

1 INDICATIONS AND USAGE

WELLBUTRIN SR (bupropion hydrochloride) is indicated for the treatment of major depressive disorder (MDD), as defined by the Diagnostic and Statistical Manual (DSM).

The efficacy of bupropion in the treatment of a major depressive episode was established in two 4-week controlled inpatient trials and one 6-week controlled outpatient trial of adult subjects with MDD [see Clinical Studies (14)].

The efficacy of WELLBUTRIN SR in maintaining an antidepressant response for up to 44 weeks following 8 weeks of acute treatment was demonstrated in a placebo‑controlled trial [see Clinical Studies (14)].

2 DOSAGE AND ADMINISTRATION

2.1 General Instructions for Use

To minimize the risk of seizure, increase the dose gradually [see Warnings and Precautions (5.3)]. WELLBUTRIN SR tablets should be swallowed whole and not crushed, divided, or chewed. WELLBUTRIN SR may be taken with or without food.

The usual adult target dose for WELLBUTRIN SR is 300 mg/day, given as 150 mg twice daily. Initiate dosing with 150 mg/day given as a single daily dose in the morning. After 3 days of dosing, the dose may be increased to the 300-mg/day target dose, given as 150 mg twice daily. There should be an interval of at least 8 hours between successive doses. A maximum of 400 mg/day, given as 200 mg twice daily, may be considered for patients in whom no clinical improvement is noted after several weeks of treatment at 300 mg/day. To avoid high peak concentrations of bupropion and/or its metabolites, do not exceed 200 mg in any single dose.

It is generally agreed that acute episodes of depression require several months or longer of antidepressant drug treatment beyond the response in the acute episode. It is unknown whether the dose of WELLBUTRIN SR needed for maintenance treatment is identical to the dose that provided an initial response. Periodically reassess the need for maintenance treatment and the appropriate dose for such treatment.

2.2 Dose Adjustment in Patients with Hepatic Impairment

In patients with moderate to severe hepatic impairment (Child-Pugh score: 7 to 15), the maximum dose of WELLBUTRIN SR is 100 mg/day or 150 mg every other day. In patients with mild hepatic impairment (Child-Pugh score: 5 to 6), consider reducing the dose and/or frequency of dosing [see Use in Specific Populations (8.7), Clinical Pharmacology (12.3)].

2.3 Dose Adjustment in Patients with Renal Impairment

Consider reducing the dose and/or frequency of WELLBUTRIN SR in patients with renal impairment (Glomerular Filtration Rate [GFR] less than 90 mL/min) [see Use in Specific Populations (8.6), Clinical Pharmacology (12.3)].

2.4 Switching a Patient to or from a Monoamine Oxidase Inhibitor (MAOI) Antidepressant

At least 14 days should elapse between discontinuation of an MAOI intended to treat depression and initiation of therapy with WELLBUTRIN SR. Conversely, at least 14 days should be allowed after stopping WELLBUTRIN SR before starting an MAOI antidepressant [see Contraindications (4), Drug Interactions (7.6)].

2.5 Use of WELLBUTRIN SR with Reversible MAOIs Such as Linezolid or Methylene Blue

Do not start WELLBUTRIN SR in a patient who is being treated with a reversible MAOI such as linezolid or intravenous methylene blue. Drug interactions can increase the risk of hypertensive reactions. In a patient who requires more urgent treatment of a psychiatric condition, non-pharmacological interventions, including hospitalization, should be considered [see Contraindications (4), Drug Interactions (7.6)].

In some cases, a patient already receiving therapy with WELLBUTRIN SR may require urgent treatment with linezolid or intravenous methylene blue. If acceptable alternatives to linezolid or intravenous methylene blue treatment are not available and the potential benefits of linezolid or intravenous methylene blue treatment are judged to outweigh the risks of hypertensive reactions in a particular patient, WELLBUTRIN SR should be stopped promptly, and linezolid or intravenous methylene blue can be administered. The patient should be monitored for 2 weeks or until 24 hours after the last dose of linezolid or intravenous methylene blue, whichever comes first. Therapy with WELLBUTRIN SR may be resumed 24 hours after the last dose of linezolid or intravenous methylene blue.

The risk of administering methylene blue by non-intravenous routes (such as oral tablets or by local injection) or in intravenous doses much lower than 1 mg/kg with WELLBUTRIN SR is unclear. The clinician should, nevertheless, be aware of the possibility of a drug interaction with such use [see Contraindications (4), Drug Interactions (7.6)].

3 DOSAGE FORMS AND STRENGTHS

- 100 mg – blue, round, biconvex, film‑coated, sustained-release tablets printed with “WELLBUTRIN SR 100”.
- 150 mg – purple, round, biconvex, film‑coated, sustained-release tablets printed with “WELLBUTRIN SR 150”.
- 200 mg – light pink, round, biconvex, film-coated, sustained-release tablets printed with “WELLBUTRIN SR 200”.

4 CONTRAINDICATIONS

- WELLBUTRIN SR is contraindicated in patients with a seizure disorder.
- WELLBUTRIN SR is contraindicated in patients with a current or prior diagnosis of bulimia or anorexia nervosa as a higher incidence of seizures was observed in such patients treated with the immediate‑release formulation of bupropion [see Warnings and Precautions (5.3)].
- WELLBUTRIN SR is contraindicated in patients undergoing abrupt discontinuation of alcohol, benzodiazepines, barbiturates, and antiepileptic drugs [see Warnings and Precautions (5.3), Drug Interactions (7.3)].
- The use of MAOIs (intended to treat psychiatric disorders) concomitantly with WELLBUTRIN SR or within 14 days of discontinuing treatment with WELLBUTRIN SR is contraindicated. There is an increased risk of hypertensive reactions when WELLBUTRIN SR is used concomitantly with MAOIs. The use of WELLBUTRIN SR within 14 days of discontinuing treatment with an MAOI is also contraindicated. Starting WELLBUTRIN SR in a patient treated with reversible MAOIs such as linezolid or intravenous methylene blue is contraindicated [see Dosage and Administration (2.4, 2.5), Warnings and Precautions (5.4), Drug Interactions (7.6)].
- WELLBUTRIN SR is contraindicated in patients with known hypersensitivity to bupropion or other ingredients of WELLBUTRIN SR. Anaphylactoid/anaphylactic reactions and Stevens-Johnson syndrome have been reported [see Warnings and Precautions (5.8)].

5 WARNINGS AND PRECAUTIONS

5.1 Suicidal Thoughts and Behaviors in Children, Adolescents, and Young Adults

Patients with MDD, both adult and pediatric, may experience worsening of their depression and/or the emergence of suicidal ideation and behavior (suicidality) or unusual changes in behavior, whether or not they are taking antidepressant medications, and this risk may persist until significant remission occurs. Suicide is a known risk of depression and certain other psychiatric disorders, and these disorders themselves are the strongest predictors of suicide. There has been a long-standing concern that antidepressants may have a role in inducing worsening of depression and the emergence of suicidality in certain patients during the early phases of treatment.

Pooled analyses of short-term placebo-controlled trials of antidepressant drugs (selective serotonin reuptake inhibitors [SSRIs] and others) show that these drugs increase the risk of suicidal thinking and behavior (suicidality) in children, adolescents, and young adults (ages 18 to 24) with MDD and other psychiatric disorders. Short-term clinical trials did not show an increase in the risk of suicidality with antidepressants compared with placebo in adults beyond age 24; there was a reduction with antidepressants compared with placebo in adults aged 65 and older.

The pooled analyses of placebo-controlled trials in children and adolescents with MDD, obsessive compulsive disorder (OCD), or other psychiatric disorders included a total of 24 short‑term trials of 9 antidepressant drugs in over 4,400 subjects. The pooled analyses of placebo‑controlled trials in adults with MDD or other psychiatric disorders included a total of 295 short‑term trials (median duration of 2 months) of 11 antidepressant drugs in over 77,000 subjects. There was considerable variation in risk of suicidality among drugs, but a tendency toward an increase in the younger subjects for almost all drugs studied. There were differences in absolute risk of suicidality across the different indications, with the highest incidence in MDD. The risk differences (drug vs. placebo), however, were relatively stable within age strata and across indications. These risk differences (drug-placebo difference in the number of cases of suicidality per 1,000 subjects treated) are provided in Table 1.

Table 1. Risk Differences in the Number of Suicidality Cases by Age Group in the Pooled Placebo-Controlled Trials of Antidepressants in Pediatric and Adult Subjects
Age Range | Drug-Placebo Difference in Number of Cases of Suicidality per 1,000 Subjects Treated
Increases Compared with Placebo
<18 | 14 additional cases
18-24 | 5 additional cases
Decreases Compared with Placebo
25-64 | 1 fewer case
≥65 | 6 fewer cases

No suicides occurred in any of the pediatric trials. There were suicides in the adult trials, but the number was not sufficient to reach any conclusion about drug effect on suicide.

It is unknown whether the suicidality risk extends to longer-term use, i.e., beyond several months. However, there is substantial evidence from placebo-controlled maintenance trials in adults with depression that the use of antidepressants can delay the recurrence of depression.

All patients being treated with antidepressants for any indication should be monitored appropriately and observed closely for clinical worsening, suicidality, and unusual changes in behavior, especially during the initial few months of a course of drug therapy, or at times of dose changes, either increases or decreases [see Boxed Warning].

The following symptoms: anxiety, agitation, panic attacks, insomnia, irritability, hostility, aggressiveness, impulsivity, akathisia (psychomotor restlessness), hypomania, and mania, have been reported in adult and pediatric patients being treated with antidepressants for major depressive disorder as well as for other indications, both psychiatric and nonpsychiatric. Although a causal link between the emergence of such symptoms and either the worsening of depression and/or the emergence of suicidal impulses has not been established, there is concern that such symptoms may represent precursors to emerging suicidality.

Consideration should be given to changing the therapeutic regimen, including possibly discontinuing the medication, in patients whose depression is persistently worse, or who are experiencing emergent suicidality or symptoms that might be precursors to worsening depression or suicidality, especially if these symptoms are severe, abrupt in onset, or were not part of the patient’s presenting symptoms.

Families and caregivers of patients being treated with antidepressants for MDD or other indications, both psychiatric and nonpsychiatric, should be alerted about the need to monitor patients for the emergence of agitation, irritability, unusual changes in behavior, and the other symptoms described above, as well as the emergence of suicidality, and to report such symptoms immediately to healthcare providers. Such monitoring should include daily observation by families and caregivers. Prescriptions for WELLBUTRIN SR should be written for the smallest quantity of tablets consistent with good patient management, in order to reduce the risk of overdose.

5.2 Neuropsychiatric Adverse Events and Suicide Risk in Smoking Cessation Treatment

WELLBUTRIN SR is not approved for smoking cessation treatment; however, it contains the same active ingredient as the smoking cessation medication ZYBAN. Serious neuropsychiatric adverse events have been reported in patients taking bupropion for smoking cessation. These postmarketing reports have included changes in mood (including depression and mania), psychosis, hallucinations, paranoia, delusions, homicidal ideation, aggression, hostility, agitation, anxiety, and panic, as well as suicidal ideation, suicide attempt, and completed suicide [see Adverse Reactions (6.2)]. Some patients who stopped smoking may have been experiencing symptoms of nicotine withdrawal, including depressed mood. Depression, rarely including suicidal ideation, has been reported in smokers undergoing a smoking cessation attempt without medication. However, some of these adverse events occurred in patients taking bupropion who continued to smoke.

Neuropsychiatric adverse events occurred in patients without and with pre-existing psychiatric disease; some patients experienced worsening of their psychiatric illnesses. Observe patients for the occurrence of neuropsychiatric adverse events. Advise patients and caregivers that the patient should stop taking WELLBUTRIN and contact a healthcare provider immediately if agitation, depressed mood, or changes in behavior or thinking that are not typical for the patient are observed, or if the patient develops suicidal ideation or suicidal behavior. In many postmarketing cases, resolution of symptoms after discontinuation of bupropion was reported. However, the symptoms persisted in some cases; therefore, ongoing monitoring and supportive care should be provided until symptoms resolve.

5.3 Seizure

WELLBUTRIN SR can cause seizure. The risk of seizure is dose-related. The dose should not exceed 400 mg/day. Increase the dose gradually. Discontinue WELLBUTRIN SR and do not restart treatment if the patient experiences a seizure.

The risk of seizures is also related to patient factors, clinical situations, and concomitant medications that lower the seizure threshold. Consider these risks before initiating treatment with WELLBUTRIN SR. WELLBUTRIN SR is contraindicated in patients with a seizure disorder, current or prior diagnosis of anorexia nervosa or bulimia, or undergoing abrupt discontinuation of alcohol, benzodiazepines, barbiturates, and antiepileptic drugs [see Contraindications (4), Drug Interactions (7.3)]. The following conditions can also increase the risk of seizure: severe head injury; arteriovenous malformation; CNS tumor or CNS infection; severe stroke; concomitant use of other medications that lower the seizure threshold (e.g., other bupropion products, antipsychotics, tricyclic antidepressants, theophylline, and systemic corticosteroids); metabolic disorders (e.g., hypoglycemia, hyponatremia, severe hepatic impairment, and hypoxia); use of illicit drugs (e.g., cocaine); or abuse or misuse of prescription drugs such as CNS stimulants. Additional predisposing conditions include diabetes mellitus treated with oral hypoglycemic drugs or insulin; use of anorectic drugs; and excessive use of alcohol, benzodiazepines, sedative/hypnotics, or opiates.

Incidence of Seizure with Bupropion Use

When WELLBUTRIN SR is dosed up to 300 mg/day, the incidence of seizure is approximately 0.1% (1/1,000) and increases to approximately 0.4% (4/1,000) at the maximum recommended dose of 400 mg/day.

The risk of seizure can be reduced if the dose of WELLBUTRIN SR does not exceed 400 mg/day, given as 200 mg twice daily, and the titration rate is gradual.

5.4 Hypertension

Treatment with WELLBUTRIN SR can result in elevated blood pressure and hypertension. Assess blood pressure before initiating treatment with WELLBUTRIN SR and monitor periodically during treatment. The risk of hypertension is increased if WELLBUTRIN SR is used concomitantly with MAOIs or other drugs that increase dopaminergic or noradrenergic activity [see Contraindications (4)].

Data from a comparative trial of the sustained-release formulation of bupropion HCl, nicotine transdermal system (NTS), the combination of sustained-release bupropion plus NTS, and placebo as an aid to smoking cessation suggest a higher incidence of treatment-emergent hypertension in patients treated with the combination of sustained-release bupropion and NTS. In this trial, 6.1% of subjects treated with the combination of sustained-release bupropion and NTS had treatment‑emergent hypertension compared with 2.5%, 1.6%, and 3.1% of subjects treated with sustained-release bupropion, NTS, and placebo, respectively. The majority of these subjects had evidence of pre-existing hypertension. Three subjects (1.2%) treated with the combination of sustained-release bupropion and NTS and 1 subject (0.4%) treated with NTS had study medication discontinued due to hypertension compared with none of the subjects treated with sustained-release bupropion or placebo. Monitoring of blood pressure is recommended in patients who receive the combination of bupropion and nicotine replacement.

In a clinical trial of bupropion immediate-release in MDD subjects with stable congestive heart failure (N = 36), bupropion was associated with an exacerbation of pre-existing hypertension in 2 subjects, leading to discontinuation of bupropion treatment. There are no controlled trials assessing the safety of bupropion in patients with a recent history of myocardial infarction or unstable cardiac disease.

5.5 Activation of Mania/Hypomania

Antidepressant treatment can precipitate a manic, mixed, or hypomanic manic episode. The risk appears to be increased in patients with bipolar disorder or who have risk factors for bipolar disorder. Prior to initiating WELLBUTRIN SR, screen patients for a history of bipolar disorder and the presence of risk factors for bipolar disorder (e.g., family history of bipolar disorder, suicide, or depression). WELLBUTRIN SR is not approved for use in treating bipolar depression.

5.6 Psychosis and Other Neuropsychiatric Reactions

Depressed patients treated with WELLBUTRIN SR have had a variety of neuropsychiatric signs and symptoms, including delusions, hallucinations, psychosis, concentration disturbance, paranoia, and confusion. Some of these patients had a diagnosis of bipolar disorder. In some cases, these symptoms abated upon dose reduction and/or withdrawal of treatment. Instruct patients to contact a healthcare professional if such reactions occur.

5.7 Angle-Closure Glaucoma

The pupillary dilation that occurs following use of many antidepressant drugs including WELLBUTRIN SR may trigger an angle-closure attack in a patient with anatomically narrow angles who does not have a patent iridectomy.

5.8 Hypersensitivity Reactions

Anaphylactoid/anaphylactic reactions have occurred during clinical trials with bupropion. Reactions have been characterized by pruritus, urticaria, angioedema, and dyspnea requiring medical treatment. In addition, there have been rare, spontaneous postmarketing reports of erythema multiforme, Stevens‑Johnson syndrome, and anaphylactic shock associated with bupropion. Instruct patients to discontinue WELLBUTRIN SR and consult a healthcare provider if they develop an allergic or anaphylactoid/anaphylactic reaction (e.g., skin rash, pruritus, hives, chest pain, edema, and shortness of breath) during treatment.

There are reports of arthralgia, myalgia, fever with rash, and other serum sickness-like symptoms suggestive of delayed hypersensitivity.

6 ADVERSE REACTIONS

The following adverse reactions are discussed in greater detail in other sections of the labeling:

- Suicidal thoughts and behaviors in adolescents and young adults [see Boxed Warning, Warnings and Precautions (5.1)]
- Neuropsychiatric symptoms and suicide risk in smoking cessation treatment [see Warnings and Precautions (5.2)]
- Seizure [see Warnings and Precautions (5.3)]
- Hypertension [see Warnings and Precautions (5.4)]
- Activation of mania or hypomania [see Warnings and Precautions (5.5)]
- Psychosis and other neuropsychiatric reactions [see Warnings and Precautions (5.6)]
- Angle-closure glaucoma [see Warnings and Precautions (5.7)]
- Hypersensitivity reactions [see Warnings and Precautions (5.8)]

6.1 Clinical Trials Experience

Because clinical trials are conducted under widely varying conditions, adverse reaction rates observed in the clinical trials of a drug cannot be directly compared with rates in the clinical trials of another drug and may not reflect the rates observed in clinical practice.

Adverse Reactions Leading to Discontinuation of Treatment

In placebo‑controlled clinical trials, 4%, 9%, and 11% of the placebo, 300‑mg/day, and 400‑mg/day groups, respectively, discontinued treatment due to adverse reactions. The specific adverse reactions leading to discontinuation in at least 1% of the 300‑mg/day or 400‑mg/day groups and at a rate at least twice the placebo rate are listed in Table 2.

Table 2. Treatment Discontinuations Due to Adverse Reactions in Placebo-Controlled Trials
Adverse Reaction | Placebo; (n = 385) | WELLBUTRIN SR 300 mg/day; (n = 376) | WELLBUTRIN SR 400 mg/day; (n = 114)
Rash | 0.0% | 2.4% | 0.9%
Nausea | 0.3% | 0.8% | 1.8%
Agitation | 0.3% | 0.3% | 1.8%
Migraine | 0.3% | 0.0% | 1.8%

Commonly Observed Adverse Reactions

Adverse reactions from Table 3 occurring in at least 5% of subjects treated with WELLBUTRIN SR and at a rate at least twice the placebo rate are listed below for the 300- and 400‑mg/day dose groups.

WELLBUTRIN SR 300 mg/day: Anorexia, dry mouth, rash, sweating, tinnitus, and tremor.

WELLBUTRIN SR 400 mg/day: Abdominal pain, agitation, anxiety, dizziness, dry mouth, insomnia, myalgia, nausea, palpitation, pharyngitis, sweating, tinnitus, and urinary frequency.

Adverse reactions reported in placebo-controlled trials are presented in Table 3. Reported adverse reactions were classified using a COSTART‑based Dictionary.

Table 3. Adverse Reactions Reported by at Least 1% of Subjects and at a Greater Frequency than Placebo in Controlled Clinical Trials
Body System/; Adverse Reaction | WELLBUTRIN SR 300 mg/day; (n = 376) | WELLBUTRIN SR 400 mg/day; (n = 114) | Placebo; (n = 385)
Body (general)
Headache | 26% | 25% | 23%
Infection | 8% | 9% | 6%
Abdominal pain | 3% | 9% | 2%
Asthenia | 2% | 4% | 2%
Chest pain | 3% | 4% | 1%
Pain | 2% | 3% | 2%
Fever | 1% | 2% | —
Cardiovascular
Palpitation | 2% | 6% | 2%
Flushing | 1% | 4% | —
Migraine | 1% | 4% | 1%
Hot flashes | 1% | 3% | 1%
Digestive
Dry mouth | 17% | 24% | 7%
Nausea | 13% | 18% | 8%
Constipation | 10% | 5% | 7%
Diarrhea | 5% | 7% | 6%
Anorexia | 5% | 3% | 2%
Vomiting | 4% | 2% | 2%
Dysphagia | 0% | 2% | 0%
Musculoskeletal
Myalgia | 2% | 6% | 3%
Arthralgia | 1% | 4% | 1%
Arthritis | 0% | 2% | 0%
Twitch | 1% | 2% | —
Nervous system
Insomnia | 11% | 16% | 6%
Dizziness | 7% | 11% | 5%
Agitation | 3% | 9% | 2%
Anxiety | 5% | 6% | 3%
Tremor | 6% | 3% | 1%
Nervousness | 5% | 3% | 3%
Somnolence | 2% | 3% | 2%
Irritability | 3% | 2% | 2%
Memory decreased | — | 3% | 1%
Paresthesia | 1% | 2% | 1%
Central nervous system stimulation | 2% | 1% | 1%
Respiratory
Pharyngitis | 3% | 11% | 2%
Sinusitis | 3% | 1% | 2%
Increased cough | 1% | 2% | 1%
Skin
Sweating | 6% | 5% | 2%
Rash | 5% | 4% | 1%
Pruritus | 2% | 4% | 2%
Urticaria | 2% | 1% | 0%
Special senses
Tinnitus | 6% | 6% | 2%
Taste perversion | 2% | 4% | —
Blurred vision or diplopia | 3% | 2% | 2%
Urogenital
Urinary frequency | 2% | 5% | 2%
Urinary urgency | — | 2% | 0%
Vaginal hemorrhagea | 0% | 2% | —
Urinary tract infection | 1% | 0% | —
a Incidence based on the number of female subjects.
— Hyphen denotes adverse events occurring in greater than 0 but less than 0.5% of subjects.

Other Adverse Reactions Observed during the Clinical Development of Bupropion

In addition to the adverse reactions noted above, the following adverse reactions have been reported in clinical trials with the sustained‑release formulation of bupropion in depressed subjects and in nondepressed smokers, as well as in clinical trials with the immediate‑release formulation of bupropion.

Adverse reaction frequencies represent the proportion of subjects who experienced a treatment‑emergent adverse reaction on at least one occasion in placebo‑controlled trials for depression (n = 987) or smoking cessation (n = 1,013), or subjects who experienced an adverse reaction requiring discontinuation of treatment in an open‑label surveillance trial with WELLBUTRIN SR (n = 3,100). All treatment‑emergent adverse reactions are included except those listed in Table 3, those listed in other safety‑related sections of the prescribing information, those subsumed under COSTART terms that are either overly general or excessively specific so as to be uninformative, those not reasonably associated with the use of the drug, and those that were not serious and occurred in fewer than 2 subjects.

Adverse reactions are further categorized by body system and listed in order of decreasing frequency according to the following definitions of frequency: Frequent adverse reactions are defined as those occurring in at least 1/100 subjects. Infrequent adverse reactions are those occurring in 1/100 to 1/1,000 subjects, while rare events are those occurring in less than 1/1,000 subjects.

Body (General): Infrequent were chills, facial edema, and photosensitivity. Rare was malaise.

Cardiovascular: Infrequent were postural hypotension, stroke, tachycardia, and vasodilation. Rare were syncope and myocardial infarction.

Digestive: Infrequent were abnormal liver function, bruxism, gastric reflux, gingivitis, increased salivation, jaundice, mouth ulcers, stomatitis, and thirst. Rare was edema of tongue.

Hemic and Lymphatic: Infrequent was ecchymosis.

Metabolic and Nutritional: Infrequent were edema and peripheral edema.

Musculoskeletal: Infrequent were leg cramps.

Nervous System: Infrequent were abnormal coordination, decreased libido, depersonalization, dysphoria, emotional lability, hostility, hyperkinesia, hypertonia, hypesthesia, suicidal ideation, and vertigo. Rare were amnesia, ataxia, derealization, and hypomania.

Respiratory: Rare was bronchospasm.

Special Senses: Infrequent were accommodation abnormality and dry eye.

Urogenital: Infrequent were impotence, polyuria, and prostate disorder.

Changes in Body Weight

In placebo‑controlled trials, subjects experienced weight gain or weight loss as shown in Table 4.

Table 4. Incidence of Weight Gain and Weight Loss (≥5 lbs.) in Placebo-Controlled Trials
Weight Change | WELLBUTRIN SR 300 mg/day; (n = 339) | WELLBUTRIN SR 400 mg/day; (n = 112) | Placebo; (n = 347)
Gained >5 lbs. | 3% | 2% | 4%
Lost >5 lbs. | 14% | 19% | 6%

In clinical trials conducted with the immediate‑release formulation of bupropion, 35% of subjects receiving tricyclic antidepressants gained weight, compared with 9% of subjects treated with the immediate‑release formulation of bupropion. If weight loss is a major presenting sign of a patient’s depressive illness, the anorectic and/or weight‑reducing potential of WELLBUTRIN SR should be considered.

6.2 Postmarketing Experience

The following adverse reactions have been identified during postapproval use of WELLBUTRIN SR and are not described elsewhere in the label. Because these reactions are reported voluntarily from a population of uncertain size, it is not always possible to reliably estimate their frequency or establish a causal relationship to drug exposure.

Body (General)

Arthralgia, myalgia, and fever with rash and other symptoms suggestive of delayed hypersensitivity. These symptoms may resemble serum sickness [see Warnings and Precautions (5.8)].

Cardiovascular

Complete atrioventricular block, extrasystoles, hypotension, hypertension (in some cases severe), phlebitis, pulmonary embolism, and Brugada pattern/syndrome.

Digestive

Colitis, esophagitis, gastrointestinal hemorrhage, gum hemorrhage, hepatitis, intestinal perforation, pancreatitis, and stomach ulcer.

Endocrine

Hyperglycemia, hypoglycemia, hyponatremia, and syndrome of inappropriate antidiuretic hormone secretion.

Hemic and Lymphatic

Anemia, leukocytosis, leukopenia, lymphadenopathy, pancytopenia, and thrombocytopenia. Altered PT and/or INR, infrequently associated with hemorrhagic or thrombotic complications, were observed when bupropion was coadministered with warfarin.

Metabolic and Nutritional

Glycosuria.

Musculoskeletal

Muscle rigidity/fever/rhabdomyolysis and muscle weakness.

Nervous System

Abnormal electroencephalogram (EEG), aggression, akinesia, aphasia, coma, completed suicide, delirium, delusions, dysarthria, euphoria, extrapyramidal syndrome (dyskinesia, dystonia, hypokinesia, parkinsonism), hallucinations, increased libido, manic reaction, neuralgia, neuropathy, paranoid ideation, restlessness, suicide attempt, unmasking tardive dyskinesia, and aseptic meningitis.

Respiratory

Pneumonia.

Skin and Subcutaneous Tissue Disorders

Alopecia, angioedema, exfoliative dermatitis, hirsutism, Stevens-Johnson syndrome, acute generalized exanthematous pustulosis, and drug reaction with eosinophilia and systemic symptoms (DRESS).

Special Senses

Deafness, increased intraocular pressure, and mydriasis.

Urogenital

Abnormal ejaculation, cystitis, dyspareunia, dysuria, gynecomastia, menopause, painful erection, salpingitis, urinary incontinence, urinary retention, and vaginitis.

7 DRUG INTERACTIONS

7.1 Potential for Other Drugs to Affect WELLBUTRIN SR

Bupropion is primarily metabolized to hydroxybupropion by CYP2B6. Therefore, the potential exists for drug interactions between WELLBUTRIN SR and drugs that are inhibitors or inducers of CYP2B6.

Inhibitors of CYP2B6

Ticlopidine and Clopidogrel: Concomitant treatment with these drugs can increase bupropion exposure but decrease hydroxybupropion exposure. Based on clinical response, dosage adjustment of WELLBUTRIN SR may be necessary when coadministered with CYP2B6 inhibitors (e.g., ticlopidine or clopidogrel) [see Clinical Pharmacology (12.3)].

Inducers of CYP2B6

Ritonavir, Lopinavir, and Efavirenz: Concomitant treatment with these drugs can decrease bupropion and hydroxybupropion exposure. Dosage increase of WELLBUTRIN SR may be necessary when coadministered with ritonavir, lopinavir, or efavirenz [see Clinical Pharmacology (12.3)] but should not exceed the maximum recommended dose.

Carbamazepine, Phenobarbital, Phenytoin: While not systematically studied, these drugs may induce the metabolism of bupropion and may decrease bupropion exposure [see Clinical Pharmacology (12.3)]. If bupropion is used concomitantly with a CYP inducer, it may be necessary to increase the dose of bupropion, but the maximum recommended dose should not be exceeded.

7.2 Potential for WELLBUTRIN SR to Affect Other Drugs

Drugs Metabolized by CYP2D6

Bupropion and its metabolites (erythrohydrobupropion, threohydrobupropion, hydroxybupropion) are CYP2D6 inhibitors. Therefore, coadministration of WELLBUTRIN SR with drugs that are metabolized by CYP2D6 can increase the exposures of drugs that are substrates of CYP2D6. Such drugs include certain antidepressants (e.g., venlafaxine, nortriptyline, imipramine, desipramine, paroxetine, fluoxetine, and sertraline), antipsychotics (e.g., haloperidol, risperidone, thioridazine), beta-blockers (e.g., metoprolol), and Type 1C antiarrhythmics (e.g., propafenone and flecainide). When used concomitantly with WELLBUTRIN SR, it may be necessary to decrease the dose of these CYP2D6 substrates, particularly for drugs with a narrow therapeutic index.

Drugs that require metabolic activation by CYP2D6 to be effective (e.g., tamoxifen) theoretically could have reduced efficacy when administered concomitantly with inhibitors of CYP2D6 such as bupropion. Patients treated concomitantly with WELLBUTRIN SR and such drugs may require increased doses of the drug [see Clinical Pharmacology (12.3)].

Digoxin

Coadministration of WELLBUTRIN SR with digoxin may decrease plasma digoxin levels. Monitor plasma digoxin levels in patients treated concomitantly with WELLBUTRIN SR and digoxin [see Clinical Pharmacology (12.3)].

7.3 Drugs that Lower Seizure Threshold

Use extreme caution when coadministering WELLBUTRIN SR with other drugs that lower seizure threshold (e.g., other bupropion products, antipsychotics, antidepressants, theophylline, or systemic corticosteroids). Use low initial doses and increase the dose gradually [see Contraindications (4), Warnings and Precautions (5.3)].

7.4 Dopaminergic Drugs (Levodopa and Amantadine)

Bupropion, levodopa, and amantadine have dopamine agonist effects. CNS toxicity has been reported when bupropion was coadministered with levodopa or amantadine. Adverse reactions have included restlessness, agitation, tremor, ataxia, gait disturbance, vertigo, and dizziness. It is presumed that the toxicity results from cumulative dopamine agonist effects. Use caution when administering WELLBUTRIN SR concomitantly with these drugs.

7.5 Use with Alcohol

In postmarketing experience, there have been rare reports of adverse neuropsychiatric events or reduced alcohol tolerance in patients who were drinking alcohol during treatment with WELLBUTRIN SR. The consumption of alcohol during treatment with WELLBUTRIN SR should be minimized or avoided.

7.6 MAO Inhibitors

Bupropion inhibits the reuptake of dopamine and norepinephrine. Concomitant use of MAOIs and bupropion is contraindicated because there is an increased risk of hypertensive reactions if bupropion is used concomitantly with MAOIs. Studies in animals demonstrate that the acute toxicity of bupropion is enhanced by the MAO inhibitor phenelzine. At least 14 days should elapse between discontinuation of an MAOI intended to treat depression and initiation of treatment with WELLBUTRIN SR. Conversely, at least 14 days should be allowed after stopping WELLBUTRIN SR before starting an MAOI antidepressant [see Dosage and Administration (2.4, 2.5), Contraindications (4)].

7.7 Drug-Laboratory Test Interactions

False-positive urine immunoassay screening tests for amphetamines have been reported in patients taking bupropion. This is due to lack of specificity of some screening tests. False-positive test results may result even following discontinuation of bupropion therapy. Confirmatory tests, such as gas chromatography/mass spectrometry, will distinguish bupropion from amphetamines.

8 USE IN SPECIFIC POPULATIONS

8.1 Pregnancy

Pregnancy Exposure Registry

There is an independent pregnancy exposure registry that monitors pregnancy outcomes in women exposed to any antidepressants during pregnancy. Healthcare providers are encouraged to register patients by calling the National Pregnancy Registry for Antidepressants at 1-844-405-6185 or visiting online at https://womensmentalhealth.org/research/pregnancyregistry/antidepressants/.

Risk Summary

Data from epidemiological studies of pregnant women exposed to bupropion in the first trimester have not identified an increased risk of congenital malformations overall (see Data). There are risks to the mother associated with untreated depression in pregnancy (see Clinical Considerations). When bupropion was administered to pregnant rats during organogenesis, there was no evidence of fetal malformations at doses up to approximately 11 times the maximum recommended human dose (MRHD) of 400 mg/day. When given to pregnant rabbits during organogenesis, non-dose–related increases in incidence of fetal malformations, and skeletal variations were observed at doses approximately equal to the MRHD and greater. Decreased fetal weights were seen at doses twice the MRHD and greater (see Animal Data).

The estimated background risk for major birth defects and miscarriage is unknown for the indicated population. All pregnancies have a background risk of birth defect, loss, or other adverse outcomes. In the U.S. general population, the estimated background risk of major birth defects and of miscarriage in clinically recognized pregnancies is 2% to 4% and 15% to 20%, respectively.

Clinical Considerations

Disease-Associated Maternal and/or Embryo/Fetal Risk: A prospective, longitudinal study followed 201 pregnant women with a history of major depressive disorder who were euthymic and taking antidepressants during pregnancy at the beginning of pregnancy. The women who discontinued antidepressants during pregnancy were more likely to experience a relapse of major depression than women who continued antidepressants. Consider the risks to the mother of untreated depression and potential effects on the fetus when discontinuing or changing treatment with antidepressant medications during pregnancy and postpartum.

Data

Human Data: Data from the international bupropion Pregnancy Registry (675 first trimester exposures) and a retrospective cohort study using the United Healthcare database (1,213 first trimester exposures) did not show an increased risk for malformations overall. The Registry was not designed or powered to evaluate specific defects but suggested a possible increase in cardiac malformations.

No increased risk for cardiovascular malformations overall has been observed after bupropion exposure during the first trimester. The prospectively observed rate of cardiovascular malformations in pregnancies with exposure to bupropion in the first trimester from the international Pregnancy Registry was 1.3% (9 cardiovascular malformations/675 first trimester maternal bupropion exposures), which is similar to the background rate of cardiovascular malformations (approximately 1%). Data from the United Healthcare database, which had a limited number of exposed cases with cardiovascular malformations, and a case-control study (6,853 infants with cardiovascular malformations and 5,763 with non-cardiovascular malformations) of self-reported bupropion use from the National Birth Defects Prevention Study (NBDPS) did not show an increased risk for cardiovascular malformations overall after bupropion exposure during the first trimester.

Study findings on bupropion exposure during the first trimester and risk for left ventricular outflow tract obstruction (LVOTO) are inconsistent and do not allow conclusions regarding a possible association. The United Healthcare database lacked sufficient power to evaluate this association; the NBDPS found increased risk for LVOTO (n = 10; adjusted OR = 2.6; 95% CI: 1.2, 5.7), and the Slone Epidemiology case control study did not find increased risk for LVOTO.

Study findings on bupropion exposure during the first trimester and risk for ventricular septal defect (VSD) are inconsistent and do not allow conclusions regarding a possible association. The Slone Epidemiology Study found an increased risk for VSD following first trimester maternal bupropion exposure (n = 17; adjusted OR = 2.5; 95% CI: 1.3, 5.0) but did not find increased risk for any other cardiovascular malformations studied (including LVOTO as above). The NBDPS and United Healthcare database study did not find an association between first trimester maternal bupropion exposure and VSD.

For the findings of LVOTO and VSD, the studies were limited by the small number of exposed cases, inconsistent findings among studies, and the potential for chance findings from multiple comparisons in case control studies.

Animal Data: In studies conducted in pregnant rats and rabbits, bupropion was administered orally during the period of organogenesis at doses of up to 450 and 150 mg/kg/day, respectively (approximately 11 and 7 times the MRHD, respectively, on a mg/m^2 basis). There was no evidence of fetal malformations in rats. When given to pregnant rabbits during organogenesis, non-dose–related increases in incidence of fetal malformations and skeletal variations were observed at the lowest dose tested (25 mg/kg/day, approximately equal to the MRHD on a mg/m^2 basis) and greater. Decreased fetal weights were observed at doses of 50 mg/kg/day (approximately 2 times the MRHD on a mg/m^2 basis) and greater. No maternal toxicity was evident at doses of 50 mg/kg/day or less.

In a pre- and postnatal development study, bupropion administered orally to pregnant rats at doses of up to 150 mg/kg/day (approximately 4 times the MRHD on a mg/m^2 basis) from embryonic implantation through lactation had no effect on pup growth or development.

8.2 Lactation

Risk Summary

Data from published literature report the presence of bupropion and its metabolites in human milk (see Data). There are no data on the effects of bupropion or its metabolites on milk production. Limited data from postmarketing reports have not identified a clear association of adverse reactions in the breastfed infant. The developmental and health benefits of breastfeeding should be considered along with the mother’s clinical need for WELLBUTRIN SR and any potential adverse effects on the breastfed child from WELLBUTRIN SR or from the underlying maternal condition.

Data

In a lactation study of 10 women, levels of orally dosed bupropion and its active metabolites were measured in expressed milk. The average daily infant exposure (assuming 150 mL/kg daily consumption) to bupropion and its active metabolites was 2% of the maternal weight-adjusted dose. Postmarketing reports have described seizures in breastfed infants. The relationship of bupropion exposure and these seizures is unclear.

8.4 Pediatric Use

Safety and effectiveness in the pediatric population have not been established [see Boxed Warning, Warnings and Precautions (5.1)].

8.5 Geriatric Use

Of the approximately 6,000 subjects who participated in clinical trials with bupropion sustained-release tablets (depression and smoking cessation trials), 275 were aged ≥65 years and 47 were aged ≥75 years. In addition, several hundred subjects aged ≥65 years participated in clinical trials using the immediate-release formulation of bupropion (depression trials). No overall differences in safety or effectiveness were observed between these subjects and younger subjects. Reported clinical experience has not identified differences in responses between the elderly and younger patients, but greater sensitivity of some older individuals cannot be ruled out.

Bupropion is extensively metabolized in the liver to active metabolites, which are further metabolized and excreted by the kidneys. The risk of adverse reactions may be greater in patients with impaired renal function. Because elderly patients are more likely to have decreased renal function, it may be necessary to consider this factor in dose selection; it may be useful to monitor renal function [see Dosage and Administration (2.3), Use in Specific Populations (8.6), Clinical Pharmacology (12.3)].

8.6 Renal Impairment

Consider a reduced dose and/or dosing frequency of WELLBUTRIN SR in patients with renal impairment (GFR less than 90 mL/min). Bupropion and its metabolites are cleared renally and may accumulate in such patients to a greater extent than usual. Monitor closely for adverse reactions that could indicate high bupropion or metabolite exposures [see Dosage and Administration (2.3), Clinical Pharmacology (12.3)].

8.7 Hepatic Impairment

In patients with moderate to severe hepatic impairment (Child-Pugh score: 7 to 15), the maximum dose of WELLBUTRIN SR is 100 mg/day or 150 mg every other day. In patients with mild hepatic impairment (Child-Pugh score: 5 to 6), consider reducing the dose and/or frequency of dosing [see Dosage and Administration (2.2), Clinical Pharmacology (12.3)].

9 DRUG ABUSE AND DEPENDENCE

9.1 Controlled Substance

Bupropion is not a controlled substance.

9.2 Abuse

Humans

Controlled clinical trials conducted in normal volunteers, in subjects with a history of multiple drug abuse, and in depressed subjects showed some increase in motor activity and agitation/excitement, often typical of central stimulant activity.

In a population of individuals experienced with drugs of abuse, a single oral dose of 400 mg of bupropion produced mild amphetamine‑like activity as compared with placebo on the Morphine‑Benzedrine Subscale of the Addiction Research Center Inventories (ARCI) and a score greater than placebo but less than 15 mg of the Schedule II stimulant dextroamphetamine on the Liking Scale of the ARCI. These scales measure general feelings of euphoria and drug liking which are often associated with abuse potential.

Findings in clinical trials, however, are not known to reliably predict the abuse potential of drugs. Nonetheless, evidence from single‑dose trials does suggest that the recommended daily dosage of bupropion when administered orally in divided doses is not likely to be significantly reinforcing to amphetamine or CNS stimulant abusers. However, higher doses (which could not be tested because of the risk of seizure) might be modestly attractive to those who abuse CNS stimulant drugs.

WELLBUTRIN SR is intended for oral use only. The inhalation of crushed tablets or injection of dissolved bupropion has been reported. Seizures and/or cases of death have been reported when bupropion has been administered intranasally or by parenteral injection.

Animals

Studies in rodents and primates demonstrated that bupropion exhibits some pharmacologic actions common to psychostimulants. In rodents, it has been shown to increase locomotor activity, elicit a mild stereotyped behavior response, and increase rates of responding in several schedule‑controlled behavior paradigms. In primate models assessing the positive-reinforcing effects of psychoactive drugs, bupropion was self-administered intravenously. In rats, bupropion produced amphetamine-like and cocaine-like discriminative stimulus effects in drug discrimination paradigms used to characterize the subjective effects of psychoactive drugs.

10 OVERDOSAGE

10.1 Human Overdose Experience

Overdoses of up to 30 grams or more of bupropion have been reported. Seizure was reported in approximately one-third of all cases. Other serious reactions reported with overdoses of bupropion alone included hallucinations, loss of consciousness, mental status changes, sinus tachycardia, ECG changes such as conduction disturbances (including QRS prolongation) or arrhythmias, clonus, myoclonus, and hyperreflexia. Fever, muscle rigidity, rhabdomyolysis, hypotension, stupor, coma, and respiratory failure have been reported mainly when bupropion was part of multiple drug overdoses.

Although most patients recovered without sequelae, deaths associated with overdoses of bupropion alone have been reported in patients ingesting large doses of the drug. Multiple uncontrolled seizures, bradycardia, cardiac failure, and cardiac arrest prior to death were reported in these patients.

10.2 Overdosage Management

Consult a Certified Poison Control Center for up-to-date guidance and advice. Call 1-800-222-1222 or refer to www.poison.org.

There are no known antidotes for bupropion. In case of an overdose, provide supportive care, including close medical supervision and monitoring. Consider the possibility of multiple drug overdose. Ensure an adequate airway, oxygenation, and ventilation. Monitor cardiac rhythm and vital signs. Induction of emesis is not recommended.

11 DESCRIPTION

WELLBUTRIN SR (bupropion hydrochloride), an antidepressant of the aminoketone class, is chemically unrelated to tricyclic, tetracyclic, selective serotonin re‑uptake inhibitor, or other known antidepressant agents. Its structure closely resembles that of diethylpropion; it is related to phenylethylamines. It is designated as (±)-1-(3-chlorophenyl)-2-[(1,1-dimethylethyl)amino]-1-propanone hydrochloride. The molecular weight is 276.2. The molecular formula is C13H18ClNO•HCl. Bupropion hydrochloride powder is white, crystalline, and highly soluble in water. It has a bitter taste and produces the sensation of local anesthesia on the oral mucosa. The structural formula is:

WELLBUTRIN SR is supplied for oral administration as 100‑mg (blue), 150‑mg (purple), and 200‑mg (light pink), film‑coated, sustained‑release tablets. Each tablet contains the labeled amount of bupropion hydrochloride and the inactive ingredients: carnauba wax, cysteine hydrochloride, hypromellose, magnesium stearate, microcrystalline cellulose, polyethylene glycol, polysorbate 80, and titanium dioxide and is printed with edible black ink. In addition, the 100‑mg tablet contains FD&C Blue No. 1 Lake, the 150‑mg tablet contains FD&C Blue No. 2 Lake and FD&C Red No. 40 Lake, and the 200‑mg tablet contains FD&C Red No. 40 Lake.

12 CLINICAL PHARMACOLOGY

12.1 Mechanism of Action

The exact mechanism of the antidepressant action of bupropion is not known but is presumed to be related to noradrenergic and/or dopaminergic mechanisms. Bupropion is a relatively weak inhibitor of the neuronal reuptake of norepinephrine and dopamine and does not inhibit the reuptake of serotonin. Bupropion does not inhibit monoamine oxidase.

12.3 Pharmacokinetics

Bupropion is a racemic mixture. The pharmacological activity and pharmacokinetics of the individual enantiomers have not been studied. The mean elimination half‑life (±SD) of bupropion after chronic dosing is 21 (±9) hours, and steady-state plasma concentrations of bupropion are reached within 8 days.

Absorption

The absolute bioavailability of WELLBUTRIN SR in humans has not been determined because an intravenous formulation for human use is not available. However, it appears likely that only a small proportion of any orally administered dose reaches the systemic circulation intact. In rat and dog studies, the bioavailability of bupropion ranged from 5% to 20%.

In humans, following oral administration of WELLBUTRIN SR, peak plasma concentration (Cmax) of bupropion is usually achieved within 3 hours.

In a trial comparing chronic dosing with WELLBUTRIN SR 150 mg twice daily to bupropion immediate‑release formulation 100 mg 3 times daily, the steady state Cmax for bupropion after WELLBUTRIN SR administration was approximately 85% of those achieved after bupropion immediate-release formulation administration. Exposure (AUC) to bupropion was equivalent for both formulations. Bioequivalence was also demonstrated for all three major active metabolites (i.e., hydroxybupropion, threohydrobupropion and erythrohydrobupropion) for both Cmax and AUC. Thus, at steady state, WELLBUTRIN SR given twice daily, and the immediate‑release formulation of bupropion given 3 times daily, are essentially bioequivalent for both bupropion and the 3 quantitatively important metabolites.

WELLBUTRIN SR can be taken with or without food. Bupropion Cmax and AUC were increased by 11% to 35% and 16% to 19%, respectively, when WELLBUTRIN SR was administered with food to healthy volunteers in three trials. The food effect is not considered clinically significant.

Distribution

In vitro tests show that bupropion is 84% bound to human plasma proteins at concentrations up to 200 mcg/mL. The extent of protein binding of the hydroxybupropion metabolite is similar to that for bupropion; whereas, the extent of protein binding of the threohydrobupropion metabolite is about half that seen with bupropion.

Metabolism

Bupropion is extensively metabolized in humans. Three metabolites are active: hydroxybupropion, which is formed via hydroxylation of the tert‑butyl group of bupropion, and the amino‑alcohol isomers, threohydrobupropion and erythrohydrobupropion, which are formed via reduction of the carbonyl group. In vitro findings suggest that CYP2B6 is the principal isoenzyme involved in the formation of hydroxybupropion, while cytochrome P450 enzymes are not involved in the formation of threohydrobupropion. Oxidation of the bupropion side chain results in the formation of a glycine conjugate of meta‑chlorobenzoic acid, which is then excreted as the major urinary metabolite. The potency and toxicity of the metabolites relative to bupropion have not been fully characterized. However, it has been demonstrated in an antidepressant screening test in mice that hydroxybupropion is one-half as potent as bupropion, while threohydrobupropion and erythrohydrobupropion are 5-fold less potent than bupropion. This may be of clinical importance because the plasma concentrations of the metabolites are as high as or higher than those of bupropion.

Following a single-dose administration of WELLBUTRIN SR in humans, Cmax of hydroxybupropion occurs approximately 6 hours post‑dose and is approximately 10 times the peak level of the parent drug at steady state. The elimination half‑life of hydroxybupropion is approximately 20 (±5) hours and its AUC at steady state is about 17 times that of bupropion. The times to peak concentrations for the erythrohydrobupropion and threohydrobupropion metabolites are similar to that of the hydroxybupropion metabolite. However, their elimination half‑lives are longer, 33 (±10) and 37 (±13) hours, respectively, and steady‑state AUCs are 1.5 and 7 times that of bupropion, respectively.

Bupropion and its metabolites exhibit linear kinetics following chronic administration of 300 to 450 mg/day.

Elimination

Following oral administration of 200 mg of ^14C‑bupropion in humans, 87% and 10% of the radioactive dose were recovered in the urine and feces, respectively. Only 0.5% of the oral dose was excreted as unchanged bupropion.

Specific Populations

Factors or conditions altering metabolic capacity (e.g., liver disease, congestive heart failure [CHF], age, concomitant medications, etc.) or elimination may be expected to influence the degree and extent of accumulation of the active metabolites of bupropion. The elimination of the major metabolites of bupropion may be affected by reduced renal or hepatic function because they are moderately polar compounds and are likely to undergo further metabolism or conjugation in the liver prior to urinary excretion.

Patients with Renal Impairment: There is limited information on the pharmacokinetics of bupropion in patients with renal impairment. An inter-trial comparison between normal subjects and subjects with end-stage renal failure demonstrated that the parent drug Cmax and AUC values were comparable in the 2 groups, whereas the hydroxybupropion and threohydrobupropion metabolites had a 2.3- and 2.8-fold increase, respectively, in AUC for subjects with end-stage renal failure. A second trial, comparing normal subjects and subjects with moderate‑to‑severe renal impairment (GFR 30.9 ± 10.8 mL/min), showed that after a single 150-mg dose of sustained-release bupropion, exposure to bupropion was approximately 2-fold higher in subjects with impaired renal function, while levels of the hydroxybupropion and threo/erythrohydrobupropion (combined) metabolites were similar in the 2 groups. Bupropion is extensively metabolized in the liver to active metabolites, which are further metabolized and subsequently excreted by the kidneys. The elimination of the major metabolites of bupropion may be reduced by impaired renal function. WELLBUTRIN SR should be used with caution in patients with renal impairment and a reduced frequency and/or dose should be considered [see Use in Specific Populations (8.6)].

Patients with Hepatic Impairment: The effect of hepatic impairment on the pharmacokinetics of bupropion was characterized in 2 single-dose trials, one in subjects with alcoholic liver disease and one in subjects with mild‑to-severe cirrhosis. The first trial demonstrated that the half‑life of hydroxybupropion was significantly longer in 8 subjects with alcoholic liver disease than in 8 healthy volunteers (32 ± 14 hours versus 21 ± 5 hours, respectively). Although not statistically significant, the AUCs for bupropion and hydroxybupropion were more variable and tended to be greater (by 53% to 57%) in volunteers with alcoholic liver disease. The differences in half‑life for bupropion and the other metabolites in the 2 groups were minimal.

The second trial demonstrated no statistically significant differences in the pharmacokinetics of bupropion and its active metabolites in 9 subjects with mild‑to-moderate hepatic cirrhosis compared with 8 healthy volunteers. However, more variability was observed in some of the pharmacokinetic parameters for bupropion (AUC, Cmax, and Tmax) and its active metabolites (t½) in subjects with mild‑to-moderate hepatic cirrhosis. In subjects with severe hepatic cirrhosis, significant alterations in the pharmacokinetics of bupropion and its metabolites were seen (Table 5).

Table 5. Pharmacokinetics of Bupropion and Metabolites in Patients with Severe Hepatic Cirrhosis: Ratio Relative to Healthy Matched Controls
 | Cmax | AUC | t½ | Tmaxa
Bupropion | 1.69 | 3.12 | 1.43 | 0.5 h
Hydroxybupropion | 0.31 | 1.28 | 3.88 | 19 h
Threo/erythrohydrobupropion amino alcohol | 0.69 | 2.48 | 1.96 | 20 h
a Difference.

Patients with Left Ventricular Dysfunction: During a chronic dosing trial with bupropion in 14 depressed subjects with left ventricular dysfunction (history of CHF or an enlarged heart on x-ray), there was no apparent effect on the pharmacokinetics of bupropion or its metabolites, compared with healthy volunteers.

Age: The effects of age on the pharmacokinetics of bupropion and its metabolites have not been fully characterized, but an exploration of steady‑state bupropion concentrations from several depression efficacy trials involving subjects dosed in a range of 300 to 750 mg/day, on a 3-times-daily schedule, revealed no relationship between age (18 to 83 years) and plasma concentration of bupropion. A single‑dose pharmacokinetic trial demonstrated that the disposition of bupropion and its metabolites in elderly subjects was similar to that of younger subjects. These data suggest there is no prominent effect of age on bupropion concentration; however, another single- and multiple-dose pharmacokinetics trial suggested that the elderly are at increased risk for accumulation of bupropion and its metabolites [see Use in Specific Populations (8.5)].

Male and Female Patients: Pooled analysis of bupropion pharmacokinetic data from 90 healthy male and 90 healthy female volunteers revealed no sex‑related differences in the peak plasma concentrations of bupropion. The mean systemic exposure (AUC) was approximately 13% higher in male volunteers compared with female volunteers. The clinical significance of this finding is unknown.

Smokers: The effects of cigarette smoking on the pharmacokinetics of bupropion were studied in 34 healthy male and female volunteers; 17 were chronic cigarette smokers and 17 were nonsmokers. Following oral administration of a single 150‑mg dose of bupropion, there were no statistically significant differences in Cmax, half-life, Tmax, AUC, or clearance of bupropion or its active metabolites between smokers and nonsmokers.

Drug Interaction Studies

Potential for Other Drugs to Affect WELLBUTRIN SR: In vitro studies indicate that bupropion is primarily metabolized to hydroxybupropion by CYP2B6. Therefore, the potential exists for drug interactions between WELLBUTRIN SR and drugs that are inhibitors or inducers of CYP2B6. In addition, in vitro studies suggest that paroxetine, sertraline, norfluoxetine, fluvoxamine, and nelfinavir inhibit the hydroxylation of bupropion.

Inhibitors of CYP2B6: Ticlopidine, Clopidogrel: In a trial in healthy male volunteers, clopidogrel 75 mg once daily or ticlopidine 250 mg twice daily increased exposures (Cmax and AUC) of bupropion by 40% and 60% for clopidogrel, and by 38% and 85% for ticlopidine, respectively. The exposures (Cmax and AUC) of hydroxybupropion were decreased 50% and 52%, respectively, by clopidogrel, and 78% and 84%, respectively, by ticlopidine. This effect is thought to be due to the inhibition of the CYP2B6-catalyzed bupropion hydroxylation.

Prasugrel: Prasugrel is a weak inhibitor of CYP2B6. In healthy subjects, prasugrel increased bupropion Cmax and AUC values by 14% and 18%, respectively, and decreased Cmax and AUC values of hydroxybupropion, an active metabolite of bupropion, by 32% and 24%, respectively.

Cimetidine: The threohydrobupropion metabolite of bupropion does not appear to be produced by cytochrome P450 enzymes. The effects of concomitant administration of cimetidine on the pharmacokinetics of bupropion and its active metabolites were studied in 24 healthy young male volunteers. Following oral administration of bupropion 300 mg with and without cimetidine 800 mg, the pharmacokinetics of bupropion and hydroxybupropion were unaffected. However, there were 16% and 32% increases in the AUC and Cmax, respectively, of the combined moieties of threohydrobupropion and erythrohydrobupropion.

Citalopram: Citalopram did not affect the pharmacokinetics of bupropion and its three metabolites.

Inducers of CYP2B6: Ritonavir and Lopinavir: In a healthy volunteer trial, ritonavir 100 mg twice daily reduced the AUC and Cmax of bupropion by 22% and 21%, respectively. The exposure of the hydroxybupropion metabolite was decreased by 23%, the threohydrobupropion decreased by 38%, and the erythrohydrobupropion decreased by 48%.

In a second healthy volunteer trial, ritonavir at a dose of 600 mg twice daily decreased the AUC and the Cmax of bupropion by 66% and 62%, respectively. The exposure of the hydroxybupropion metabolite was decreased by 78%, the threohydrobupropion decreased by 50%, and the erythrohydrobupropion decreased by 68%.

In another healthy volunteer trial, lopinavir 400 mg/ritonavir 100 mg twice daily decreased bupropion AUC and Cmax by 57%. The AUC and Cmax of hydroxybupropion were decreased by 50% and 31%, respectively.

Efavirenz: In a trial in healthy volunteers, efavirenz 600 mg once daily for 2 weeks reduced the AUC and Cmax of bupropion by approximately 55% and 34%, respectively. The AUC of hydroxybupropion was unchanged, whereas Cmax of hydroxybupropion was increased by 50%.

Carbamazepine, Phenobarbital, Phenytoin: While not systematically studied, these drugs may induce the metabolism of bupropion.

Potential for WELLBUTRIN SR to Affect Other Drugs

Animal data indicated that bupropion may be an inducer of drug-metabolizing enzymes in humans. In one trial, following chronic administration of bupropion 100 mg three times daily to 8 healthy male volunteers for 14 days, there was no evidence of induction of its own metabolism. Nevertheless, there may be potential for clinically important alterations of blood levels of co-administered drugs.

Drugs Metabolized by CYP2D6: In vitro, bupropion and its metabolites (erythrohydrobupropion, threohydrobupropion, hydroxybupropion) are CYP2D6 inhibitors. In a clinical trial of 15 male subjects (ages 19 to 35 years) who were extensive metabolizers of CYP2D6, bupropion 300 mg/day followed by a single dose of 50 mg desipramine increased the Cmax, AUC, and t1/2 of desipramine by an average of approximately 2-, 5-, and 2-fold, respectively. The effect was present for at least 7 days after the last dose of bupropion. Concomitant use of bupropion with other drugs metabolized by CYP2D6 has not been formally studied.

Citalopram: Although citalopram is not primarily metabolized by CYP2D6, in one trial bupropion increased the Cmax and AUC of citalopram by 30% and 40%, respectively.

Lamotrigine: Multiple oral doses of bupropion had no statistically significant effects on the single-dose pharmacokinetics of lamotrigine in 12 healthy volunteers.

Digoxin: Literature data showed that digoxin exposure was decreased when a single oral dose of 0.5-mg digoxin was administered 24 hours after a single oral dose of extended-release 150-mg bupropion in healthy volunteers.

13 NONCLINICAL TOXICOLOGY

13.1 Carcinogenesis, Mutagenesis, Impairment of Fertility

Lifetime carcinogenicity studies were performed in rats and mice at bupropion doses up to 300 and 150 mg/kg/day, respectively. These doses are approximately 7 and 2 times the MRHD, respectively, on a mg/m^2 basis. In the rat study there was an increase in nodular proliferative lesions of the liver at doses of 100 to 300 mg/kg/day (approximately 2 to 7 times the MRHD on a mg/m^2 basis); lower doses were not tested. The question of whether or not such lesions may be precursors of neoplasms of the liver is currently unresolved. Similar liver lesions were not seen in the mouse study, and no increase in malignant tumors of the liver and other organs was seen in either study.

Bupropion produced a positive response (2 to 3 times control mutation rate) in 2 of 5 strains in the Ames bacterial mutagenicity assay. Bupropion produced an increase in chromosomal aberrations in 1 of 3 in vivo rat bone marrow cytogenetic studies.

There were no effects on male and female fertility when rats were administered oral doses of bupropion up to 300 mg/kg/day (approximately 7 times the MRHD on a mg/m^2 basis) to females prior to mating and either through Day 13 of gestation or through lactation, and to males for 60 days prior to and through mating. However, doses of 200 mg/kg/day (approximately 5 times the MRHD on a mg/m^2 basis) or greater, caused transient ataxia or behavioral changes in adult female rats. There were also no adverse effects on fertility, reproduction, or growth and development of male or female offspring.

14 CLINICAL STUDIES

The efficacy of the immediate‑release formulation of bupropion in the treatment of major depressive disorder was established in two 4‑week, placebo‑controlled trials in adult inpatients with MDD (Trials 1 and 2 in Table 6) and in one 6‑week, placebo‑controlled trial in adult outpatients with MDD (Trial 3 in Table 6). In the first trial, the dose range of bupropion was 300 mg to 600 mg/day administered in divided doses; 78% of subjects were treated with doses of 300 mg to 450 mg/day. This trial demonstrated the effectiveness of the immediate‑release formulation of bupropion by the Hamilton Depression Rating Scale (HDRS) total score, the HDRS depressed mood item (Item 1), and the Clinical Global Impressions severity score (CGI-S). The second trial included 2 doses of the immediate‑release formulation of bupropion (300 and 450 mg/day) and placebo. This trial demonstrated the effectiveness of the immediate‑release formulation of bupropion, but only at the 450‑mg/day dose. The efficacy results were significant for the HDRS total score and the CGI-S score, but not for HDRS Item 1. In the third trial, outpatients were treated with 300 mg/day of the immediate‑release formulation of bupropion. This trial demonstrated the efficacy of the immediate‑release formulation of bupropion as measured by the HDRS total score, the HDRS Item 1, the Montgomery‑Asberg Depression Rating Scale (MADRS), the CGI-S score, and the CGI-Improvement Scale (CGI-I) score.

Table 6. Efficacy of Immediate-Release Bupropion for the Treatment of Major Depressive Disorder
Trial Number | Treatment Group | Primary Efficacy Measure: HDRS
Trial Number | Treatment Group | Mean Baseline Score (SD) | LS Mean Score at Endpoint Visit (SE) | Placebo-subtracted Differencea (95% CI)
Trial 1 | Immediate-Release Bupropion; 300-600 mg/dayb (n = 48) | 28.5 (5.1) | 14.9 (1.3) | -4.7 (-8.8, -0.6)
Trial 1 | Placebo (n = 27) | 29.3 (7.0) | 19.6 (1.6) | --
 |  | Mean Baseline Score (SD) | LS Mean Change from Baseline (SE) | Placebo-subtracted Differencea (95% CI)
Trial 2 | Immediate-Release Bupropion; 300 mg/day (n = 36) | 32.4 (5.9) | -15.5 (1.7) | -4.1
Trial 2 | Immediate-Release Bupropion; 450 mg/dayb (n = 34) | 34.8 (4.6) | -17.4 (1.7) | -5.9 (-10.5, -1.4)
Trial 2 | Placebo (n = 39) | 32.9 (5.4) | -11.5 (1.6) | --
Trial 3 | Immediate-Release Bupropion; 300 mg/dayb (n = 110) | 26.5 (4.3) | -12.0 (NA) | -3.9 (-5.7, -1.0)
Trial 3 | Placebo (n = 106) | 27.0 (3.5) | -8.7 (NA) | --
n: sample size; SD: standard deviation; SE: standard error; LS Mean: least-squares mean; CI: unadjusted confidence interval included for doses that were demonstrated to be effective; NA: not available.
a Difference (drug minus placebo) in least-squares estimates with respect to the primary efficacy parameter. For Trial 1, it refers to the mean score at the endpoint visit; for Trials 2 and 3, it refers to the mean change from baseline to the endpoint visit.
b Doses that are demonstrated to be statistically significantly superior to placebo.

Although there are not as yet independent trials demonstrating the antidepressant effectiveness of the sustained‑release formulation of bupropion, trials have demonstrated the bioequivalence of the immediate‑release and sustained‑release forms of bupropion under steady‑state conditions, i.e., bupropion sustained‑release 150 mg twice daily was shown to be bioequivalent to 100 mg 3 times daily of the immediate‑release formulation of bupropion, with regard to both rate and extent of absorption, for parent drug and metabolites.

In a longer-term trial, outpatients meeting DSM-IV criteria for major depressive disorder, recurrent type, who had responded during an 8-week open trial on WELLBUTRIN SR (150 mg twice daily) were randomized to continuation of their same dose of WELLBUTRIN SR or placebo for up to 44 weeks of observation for relapse. Response during the open phase was defined as CGI Improvement score of 1 (very much improved) or 2 (much improved) for each of the final 3 weeks. Relapse during the double-blind phase was defined as the investigator’s judgment that drug treatment was needed for worsening depressive symptoms. Patients receiving continued treatment with WELLBUTRIN SR experienced significantly lower relapse rates over the subsequent 44 weeks compared with those receiving placebo.

16 HOW SUPPLIED/STORAGE AND HANDLING

WELLBUTRIN SR sustained‑release tablets, 100 mg of bupropion hydrochloride, are blue, round, biconvex, film‑coated tablets printed with “WELLBUTRIN SR 100” in bottles of 60 (NDC 0173-0947-55) tablets.

WELLBUTRIN SR sustained‑release tablets, 150 mg of bupropion hydrochloride, are purple, round, biconvex, film‑coated tablets printed with “WELLBUTRIN SR 150” in bottles of 60 (NDC 0173-0135-55) tablets.

WELLBUTRIN SR sustained‑release tablets, 200 mg of bupropion hydrochloride, are light pink, round, biconvex, film‑coated tablets printed with “WELLBUTRIN SR 200” in bottles of 60 (NDC 0173-0722-00) tablets.

Store at room temperature, 20° to 25°C (68° to 77°F); excursions permitted between 15°C and 30°C (59°F and 86°F) [see USP Controlled Room Temperature]. Protect from light and moisture.

17 PATIENT COUNSELING INFORMATION

Advise the patient to read the FDA-approved patient labeling (Medication Guide).

Suicidal Thoughts and Behaviors

Instruct patients, their families, and/or their caregivers to be alert to the emergence of anxiety, agitation, panic attacks, insomnia, irritability, hostility, aggressiveness, impulsivity, akathisia (psychomotor restlessness), hypomania, mania, other unusual changes in behavior, worsening of depression, and suicidal ideation, especially early during antidepressant treatment and when the dose is adjusted up or down. Advise families and caregivers of patients to observe for the emergence of such symptoms on a day‑to‑day basis, since changes may be abrupt. Such symptoms should be reported to the patient’s prescriber or healthcare professional, especially if they are severe, abrupt in onset, or were not part of the patient’s presenting symptoms. Symptoms such as these may be associated with an increased risk for suicidal thinking and behavior and indicate a need for very close monitoring and possibly changes in the medication.

Neuropsychiatric Adverse Events and Suicide Risk in Smoking Cessation Treatment

Although WELLBUTRIN SR is not indicated for smoking cessation treatment, it contains the same active ingredient as ZYBAN which is approved for this use. Inform patients that some patients have experienced changes in mood (including depression and mania), psychosis, hallucinations, paranoia, delusions, homicidal ideation, aggression, hostility, agitation, anxiety, and panic, as well as suicidal ideation and suicide when attempting to quit smoking while taking bupropion. Instruct patients to discontinue bupropion and contact a healthcare professional if they experience such symptoms [see Warnings and Precautions (5.2), Adverse Reactions (6.2)].

Severe Allergic Reactions

Educate patients on the symptoms of hypersensitivity and to discontinue WELLBUTRIN SR if they have a severe allergic reaction.

Seizure

Instruct patients to discontinue and not restart WELLBUTRIN SR if they experience a seizure while on treatment. Advise patients that the excessive use or abrupt discontinuation of alcohol, benzodiazepines, antiepileptic drugs, or sedatives/hypnotics can increase the risk of seizure. Advise patients to minimize or avoid use of alcohol.

As the dose is increased during initial titration to doses above 150 mg/day, instruct patients to take WELLBUTRIN SR in 2 divided doses, preferably with at least 8 hours between successive doses, to minimize the risk of seizures.

Angle-Closure Glaucoma

Patients should be advised that taking WELLBUTRIN SR can cause mild pupillary dilation, which in susceptible individuals, can lead to an episode of angle-closure glaucoma. Pre-existing glaucoma is almost always open-angle glaucoma because angle-closure glaucoma, when diagnosed, can be treated definitively with iridectomy. Open-angle glaucoma is not a risk factor for angle-closure glaucoma. Patients may wish to be examined to determine whether they are susceptible to angle closure, and have a prophylactic procedure (e.g., iridectomy), if they are susceptible [see Warnings and Precautions (5.7)].

Bupropion-Containing Products

Educate patients that WELLBUTRIN SR contains the same active ingredient (bupropion hydrochloride) found in ZYBAN, which is used as an aid to smoking cessation treatment, and that WELLBUTRIN SR should not be used in combination with ZYBAN or any other medications that contain bupropion (such as WELLBUTRIN, the immediate-release formulation and WELLBUTRIN XL or FORFIVO XL, the extended-release formulations, and APLENZIN, the extended-release formulation of bupropion hydrobromide). In addition, there are a number of generic bupropion HCl products for the immediate-, sustained-, and extended-release formulations.

Potential for Cognitive and Motor Impairment

Advise patients that any CNS‑active drug like WELLBUTRIN SR may impair their ability to perform tasks requiring judgment or motor and cognitive skills. Advise patients that until they are reasonably certain that WELLBUTRIN SR does not adversely affect their performance, they should refrain from driving an automobile or operating complex, hazardous machinery. WELLBUTRIN SR may lead to decreased alcohol tolerance.

Concomitant Medications

Counsel patients to notify their healthcare provider if they are taking or plan to take any prescription or over‑the‑counter drugs because WELLBUTRIN SR sustained-release tablets and other drugs may affect each others’ metabolisms.

Pregnancy

Advise patients to notify their healthcare provider if they become pregnant or intend to become pregnant during therapy with WELLBUTRIN SR. Advise patients that there is a pregnancy exposure registry that monitors pregnancy outcomes in women exposed to WELLBUTRIN SR during pregnancy [see Use in Specific Populations (8.1)].

Storage Information

Instruct patients to store WELLBUTRIN SR at room temperature, between 68°F and 77°F (20°C to 25°C) and keep the tablets dry and out of the light.

Administration Information

Instruct patients to swallow WELLBUTRIN SR tablets whole so that the release rate is not altered. Do not chew, divide, or crush tablets; they are designed to slowly release drug in the body. When patients take more than 150 mg/day, instruct them to take WELLBUTRIN SR in 2 doses at least 8 hours apart, to minimize the risk of seizures. Instruct patients if they miss a dose, not to take an extra tablet to make up for the missed dose and to take the next tablet at the regular time because of the dose-related risk of seizure. Instruct patients that WELLBUTRIN SR tablets may have an odor. WELLBUTRIN SR can be taken with or without food.

WELLBUTRIN, WELLBUTRIN SR, WELLBUTRIN XL, and ZYBAN are trademarks owned by or licensed to the GSK group of companies. The other brands listed are trademarks owned by or licensed to their respective owners and are not owned by or licensed to the GSK group of companies. The makers of these brands are not affiliated with and do not endorse the GSK group of companies or its products.

GlaxoSmithKline

Durham, NC 27701

©2025 GSK group of companies or its licensor.

WLS:22PI

MEDICATION GUIDE

WELLBUTRIN SR (WELL byu-trin)

(bupropion hydrochloride) Sustained‑Release Tablets

IMPORTANT: Be sure to read the three sections of this Medication Guide. The first section is about the risk of suicidal thoughts and actions with antidepressant medicines; the second section is about the risk of changes in thinking and behavior, depression and suicidal thoughts or actions with medicines used to quit smoking; and the third section is entitled “What Other Important Information Should I Know About WELLBUTRIN SR?”

Antidepressant Medicines, Depression and Other Serious Mental Illnesses, and Suicidal Thoughts or Actions

This section of the Medication Guide is only about the risk of suicidal thoughts and actions with antidepressant medicines.

What is the most important information I should know about antidepressant medicines, depression and other serious mental illnesses, and suicidal thoughts or actions?

1. Antidepressant medicines may increase the risk of suicidal thoughts or actions in some children, teenagers, or young adults within the first few months of treatment.
2. Depression or other serious mental illnesses are the most important causes of suicidal thoughts and actions. Some people may have a particularly high risk of having suicidal thoughts or actions. These include people who have (or have a family history of) bipolar illness (also called manic-depressive illness) or suicidal thoughts or actions.
3. How can I watch for and try to prevent suicidal thoughts and actions in myself or a family member?
  1. Pay close attention to any changes, especially sudden changes, in mood, behaviors, thoughts, or feelings. This is very important when an antidepressant medicine is started or when the dose is changed.
  2. Call your healthcare provider right away to report new or sudden changes in mood, behavior, thoughts, or feelings.
  3. Keep all follow-up visits with your healthcare provider as scheduled. Call the healthcare provider between visits as needed, especially if you have concerns about symptoms.

Call your healthcare provider right away if you or your family member has any of the following symptoms, especially if they are new, worse, or worry you:

- thoughts about suicide or dying
- attempts to commit suicide
- new or worse depression
- new or worse anxiety
- feeling very agitated or restless
- panic attacks

- trouble sleeping (insomnia)
- new or worse irritability
- acting aggressive, being angry, or violent
- acting on dangerous impulses
- an extreme increase in activity and talking (mania)
- other unusual changes in behavior or mood

What else do I need to know about antidepressant medicines?

- Never stop an antidepressant medicine without first talking to a healthcare provider. Stopping an antidepressant medicine suddenly can cause other symptoms.
- Antidepressants are medicines used to treat depression and other illnesses. It is important to discuss all the risks of treating depression and also the risks of not treating it. Patients and their families or other caregivers should discuss all treatment choices with the healthcare provider, not just the use of antidepressants.
- Antidepressant medicines have other side effects. Talk to the healthcare provider about the side effects of the medicine prescribed for you or your family member.
- Antidepressant medicines can interact with other medicines. Know all of the medicines that you or your family member takes. Keep a list of all medicines to show the healthcare provider. Do not start new medicines without first checking with your healthcare provider.

It is not known if WELLBUTRIN SR is safe and effective in children under the age of 18.

Quitting Smoking, Quit-Smoking Medications, Changes in Thinking and Behavior, Depression, and Suicidal Thoughts or Actions

This section of the Medication Guide is only about the risk of changes in thinking and behavior, depression and suicidal thoughts or actions with drugs used to quit smoking. Although WELLBUTRIN SR is not a treatment for quitting smoking, it contains the same active ingredient (bupropion hydrochloride) as ZYBAN which is used to help patients quit smoking.

Talk to your healthcare provider or your family member’s healthcare provider about:

- all risks and benefits of quit-smoking medicines
- all treatment choices for quitting smoking

When you try to quit smoking, with or without bupropion you may have symptoms that may be due to nicotine withdrawal, including:

- urge to smoke
- depressed mood
- trouble sleeping
- irritability

- frustration
- anger
- feeling anxious
- difficulty concentrating

- restlessness
- decreased heart rate
- increased appetite
- weight gain

Some people have even experienced suicidal thoughts when trying to quit smoking without medication. Sometimes quitting smoking can lead to worsening of mental health problems that you already have, such as depression.

Some people have had serious side effect while taking bupropion to help them quit smoking, including:

New or worse mental health problems, such as changes in behavior or thinking, aggression, hostility, agitation, depression, or suicidal thoughts or actions. Some people had these symptoms when they began taking bupropion, and others developed them after several weeks of treatment, or after stopping bupropion. These symptoms happened more often in people who had a history of mental health problems before taking bupropion than in people without a history of mental health problems.

Stop taking WELLBUTRIN SR and call your healthcare provider right away if you, your family, or caregiver notice any of these symptoms. Work with your healthcare provider to decide whether you should continue to take WELLBUTRIN SR. In many people, these symptoms went away after stopping WELLBUTRIN SR, but in some people, symptoms continued after stopping WELLBUTRIN SR. It is important for you to follow-up with your healthcare provider until your symptoms go away. Before taking WELLBUTRIN SR, tell your healthcare provider if you have ever had depression or other mental health problems. You should also tell your healthcare provider about any symptoms you had during other times you tried to quit smoking, with or without bupropion.

What Other Important Information Should I Know About WELLBUTRIN SR?

- Seizures: There is a chance of having a seizure (convulsion, fit) with WELLBUTRIN SR, especially in people:
  - with certain medical problems.
  - who take certain medicines.
The chance of having seizures increases with higher doses of WELLBUTRIN SR. For more information, see the sections “Who should not take WELLBUTRIN SR?” and “What should I tell my healthcare provider before taking WELLBUTRIN SR?” Tell your healthcare provider about all of your medical conditions and all the medicines you take. Do not take any other medicines while you are taking WELLBUTRIN SR unless your healthcare provider has said it is okay to take them.
If you have a seizure while taking WELLBUTRIN SR, stop taking the tablets and call your healthcare provider right away. Do not take WELLBUTRIN SR again if you have a seizure.
- High blood pressure (hypertension). Some people get high blood pressure, that can be severe, while taking WELLBUTRIN SR. The chance of high blood pressure may be higher if you also use nicotine replacement therapy (such as a nicotine patch) to help you stop smoking (see the section of this Medication Guide called “How should I take WELLBUTRIN SR?”).
- Manic episodes. Some people may have periods of mania while taking WELLBUTRIN SR, including:
  - Greatly increased energy
  - Severe trouble sleeping
  - Racing thoughts
  - Reckless behavior
  - Unusually grand ideas
  - Excessive happiness or irritability
  - Talking more or faster than usual
If you have any of the above symptoms of mania, call your healthcare provider.
- Unusual thoughts or behaviors. Some patients have unusual thoughts or behaviors while taking WELLBUTRIN SR, including delusions (believe you are someone else), hallucinations (seeing or hearing things that are not there), paranoia (feeling that people are against you), or feeling confused. If this happens to you, call your healthcare provider.
- Visual problems.
  - eye pain
  - changes in vision
  - swelling or redness in or around the eye
Only some people are at risk for these problems. You may want to undergo an eye examination to see if you are at risk and receive preventative treatment if you are.
- Severe allergic reactions. Some people can have severe allergic reactions to WELLBUTRIN SR. Stop taking WELLBUTRIN SR and call your healthcare provider right away if you get a rash, itching, hives, fever, swollen lymph glands, painful sores in the mouth or around the eyes, swelling of the lips or tongue, chest pain, or have trouble breathing. These could be signs of a serious allergic reaction.

What is WELLBUTRIN SR?

WELLBUTRIN SR is a prescription medicine used to treat adults with a certain type of depression called major depressive disorder.

Who should not take WELLBUTRIN SR?

Do not take WELLBUTRIN SR if you

- have or had a seizure disorder or epilepsy.
- have or had an eating disorder such as anorexia nervosa or bulimia.
- are taking any other medicines that contain bupropion, including ZYBAN (used to help people stop smoking), WELLBUTRIN, WELLBUTRIN XL, APLENZIN, or FORFIVO XL. Bupropion is the same active ingredient that is in WELLBUTRIN SR.
- drink a lot of alcohol and abruptly stop drinking, or use medicines called sedatives (these make you sleepy), benzodiazepines, or anti-seizure medicines, and you stop using them all of a sudden.
- take a monoamine oxidase inhibitor (MAOI). Ask your healthcare provider or pharmacist if you are not sure if you take an MAOI, including the antibiotic linezolid.
  - do not take an MAOI within 2 weeks of stopping WELLBUTRIN SR unless directed to do so by your healthcare provider.
  - do not start WELLBUTRIN SR if you stopped taking an MAOI in the last 2 weeks unless directed to do so by your healthcare provider.
- are allergic to the active ingredient in WELLBUTRIN SR, bupropion, or to any of the inactive ingredients. See the end of this Medication Guide for a complete list of ingredients in WELLBUTRIN SR.

What should I tell my healthcare provider before taking WELLBUTRIN SR?

Tell your healthcare provider if you have ever had depression, suicidal thoughts or actions, or other mental health problems. See “Antidepressant Medicines, Depression and Other Serious Mental Illnesses, and Suicidal Thoughts or Actions.”

- Tell your healthcare provider about your other medical conditions including if you:
  - have liver problems, especially cirrhosis of the liver.
  - have kidney problems.
  - have, or have had, an eating disorder, such as anorexia nervosa or bulimia.
  - have had a head injury.
  - have had a seizure (convulsion, fit).
  - have a tumor in your nervous system (brain or spine).
  - have had a heart attack, heart problems, or high blood pressure.
  - are a diabetic taking insulin or other medicines to control your blood sugar.
  - drink alcohol.
  - abuse prescription medicines or street drugs.
  - are pregnant or plan to become pregnant. Talk to your healthcare provider about the risk to your unborn baby if you take WELLBUTRIN SR during pregnancy.
    - Tell your healthcare provider if you become pregnant or think you are pregnant during treatment with WELLBUTRIN SR.
    - If you become pregnant during treatment with WELLBUTRIN SR, talk to your healthcare provider about registering with the National Pregnancy Registry for Antidepressants. You can register by calling 1-844-405-6185.
  - are breastfeeding or plan to breastfeed during treatment with WELLBUTRIN SR. WELLBUTRIN SR passes into your milk. Talk to your healthcare provider about the best way to feed your baby during treatment with WELLBUTRIN SR.

Tell your healthcare provider about all the medicines you take, including prescription, over-the-counter medicines, vitamins, and herbal supplements. Many medicines increase your chances of having seizures or other serious side effects if you take them while you are taking WELLBUTRIN SR.

How should I take WELLBUTRIN SR?

- Take WELLBUTRIN SR exactly as prescribed by your healthcare provider. Do not change your dose or stop taking WELLBUTRIN SR without talking to your healthcare provider first.
- Swallow WELLBUTRIN SR tablets whole. Do not chew, cut, or crush WELLBUTRIN SR tablets. If you do, the medicine will be released into your body too quickly. If this happens you may be more likely to get side effects including seizures. Tell your healthcare provider if you cannot swallow tablets.
- WELLBUTRIN SR tablets may have an odor. This is normal.
- Take WELLBUTRIN SR at the same time each day.
- Take your doses of WELLBUTRIN SR at least 8 hours apart.
- You may take WELLBUTRIN SR with or without food.
- If you miss a dose, do not take an extra dose to make up for the dose you missed. Wait and take your next dose at the regular time. This is very important. Too much WELLBUTRIN SR can increase your chance of having a seizure.
- If you take too much WELLBUTRIN SR, or overdose, call your local emergency room or poison control center right away.
- Do not take any other medicines while taking WELLBUTRIN SR unless your healthcare provider has told you it is okay.
- If you are taking WELLBUTRIN SR for the treatment of major depressive disorder, it may take several weeks for you to feel that WELLBUTRIN SR is working. Once you feel better, it is important to keep taking WELLBUTRIN SR exactly as directed by your healthcare provider. Call your healthcare provider if you do not feel WELLBUTRIN SR is working for you.

What should I avoid while taking WELLBUTRIN SR?

- Limit or avoid using alcohol during treatment with WELLBUTRIN SR. If you usually drink a lot of alcohol, talk with your healthcare provider before suddenly stopping. If you suddenly stop drinking alcohol, you may increase your chance of having seizures.
- Do not drive a car or use heavy machinery until you know how WELLBUTRIN SR affects you. WELLBUTRIN SR can affect your ability to do these things safely.

What are possible side effects of WELLBUTRIN SR?

WELLBUTRIN SR can cause serious side effects. See the sections at the beginning of this Medication Guide for information about serious side effects of WELLBUTRIN.

The most common side effects of WELLBUTRIN SR include:

- headache
- dry mouth
- nausea
- trouble sleeping

- dizziness
- sore throat
- constipation

If you have nausea, take your medicine with food. If you have trouble sleeping, do not take your medicine too close to bedtime.

Tell your healthcare provider right away about any side effects that bother you.

These are not all the possible side effects of WELLBUTRIN SR. For more information, ask your healthcare provider or pharmacist.

Call your doctor for medical advice about side effects. You may report side effects to FDA at 1‑800-FDA-1088.

You may also report side effects to GlaxoSmithKline at 1-888-825-5249.

How should I store WELLBUTRIN SR?

- Store WELLBUTRIN SR at room temperature between 68°F and 77°F (20°C to 25°C).
- Keep WELLBUTRIN SR dry and out of the light.

Keep WELLBUTRIN SR and all medicines out of the reach of children.

General information about the safe and effective use of WELLBUTRIN SR.

Medicines are sometimes prescribed for purposes other than those listed in a Medication Guide. Do not use WELLBUTRIN SR for a condition for which it was not prescribed. Do not give WELLBUTRIN SR to other people, even if they have the same symptoms you have. It may harm them.

If you take a urine drug screening test, WELLBUTRIN SR may make the test result positive for amphetamines. If you tell the person giving you the drug screening test that you are taking WELLBUTRIN SR, they can do a more specific drug screening test that should not have this problem.

This Medication Guide summarizes important information about WELLBUTRIN SR. If you would like more information, talk with your healthcare provider. You can ask your healthcare provider or pharmacist for information about WELLBUTRIN SR that is written for healthcare professionals.

For more information about WELLBUTRIN SR, call 1-888-825-5249.

What are the ingredients in WELLBUTRIN SR?

Active ingredient: bupropion hydrochloride.

Inactive ingredients: carnauba wax, cysteine hydrochloride, hypromellose, magnesium stearate, microcrystalline cellulose, polyethylene glycol, polysorbate 80, and titanium dioxide. The tablets are printed with edible black ink. In addition, the 100‑mg tablet contains FD&C Blue No. 1 Lake, the 150‑mg tablet contains FD&C Blue No. 2 Lake and FD&C Red No. 40 Lake, and the 200‑mg tablet contains FD&C Red No. 40 Lake. The tablets are printed with edible black ink.

GlaxoSmithKline

Durham, NC 27701

WELLBUTRIN, WELLBUTRIN SR, WELLBUTRIN XL, and ZYBAN are trademarks owned by or licensed to the GSK group of companies. The other brands listed are trademarks owned or licensed to their respective owners and are not owned by or licensed to the GSK group of companies. The makers of these brands are not affiliated with and do not endorse the GSK group of companies or its products.

©2022 GSK group of companies or its licensor.

WLS:16MG

This Medication Guide has been approved by the U.S. Food and Drug Administration. Revised: 12/2022

PACKAGE LABEL

PRINCIPAL DISPLAY PANEL

NDC 0173-0947-55

Wellbutrin SR

(bupropion HCl)

Sustained-Release Tablets

Rx only

Twice-A-Day

(After Initial Titration)

100 mg

Each sustained-release tablet contains 100 mg bupropion HCl.

WARNING: Do not use with other medicines that contain bupropion HCl.

Federal Law requires dispensing of Wellbutrin SR with the Medication Guide provided with this bottle.

See prescribing information for dosage information.

Store at controlled room temperature, 68o to 77oF (20o to 25oC) [see USP].

Keep dry and out of light.

60 Tablets

GlaxoSmithKline

Durham, NC 27701

Made in Spain

Trademark owned or licensed by GSK.

©2023 GSK or licensor.

62000000085809 Rev. 2/23

PACKAGE LABEL

PRINCIPAL DISPLAY PANEL

NDC 0173-0135-55

Wellbutrin SR

(bupropion HCl)

Sustained-Release Tablets

Rx only

Twice-A-Day

(After Initial Titration)

150 mg

Each sustained-release tablet contains 150 mg bupropion HCl.

WARNING: Do not use with other medicines that contain bupropion HCl.

Federal Law requires dispensing of Wellbutrin SR with the Medication Guide provided with this bottle.

See prescribing information for dosage information.

Store at controlled room temperature, 68o to 77oF (20o to 25oC) [see USP].

Keep dry and out of light.

60 Tablets

GlaxoSmithKline

Durham, NC 27701

Made in Spain

Trademark owned or licensed by GSK.

©2023 GSK or licensor.

62000000085814 Rev. 2/23

PACKAGE LABEL

PRINCIPAL DISPLAY PANEL

NDC 0173-0722-00

Wellbutrin SR

(bupropion HCl)

Sustained-Release Tablets

Rx only

Twice-A-Day

(After Initial Titration)

200 mg

Each sustained-release tablet contains 200 mg bupropion HCl.

WARNING: Do not use with other medicines that contain bupropion HCl.

Federal Law requires dispensing of Wellbutrin SR with the Medication Guide provided with this bottle.

See prescribing information for dosage information.

Store at controlled room temperature, 68o to 77oF (20o to 25oC) [see USP].

Keep dry and out of light.

60 Tablets

GlaxoSmithKline

Durham, NC 27701

Made in Spain

Trademark owned or licensed by GSK.

©2023 GSK or licensor.

62000000085815 Rev. 2/23